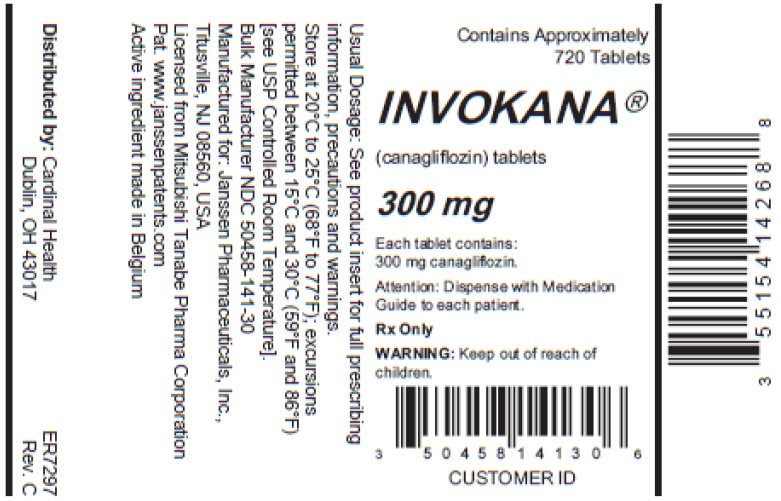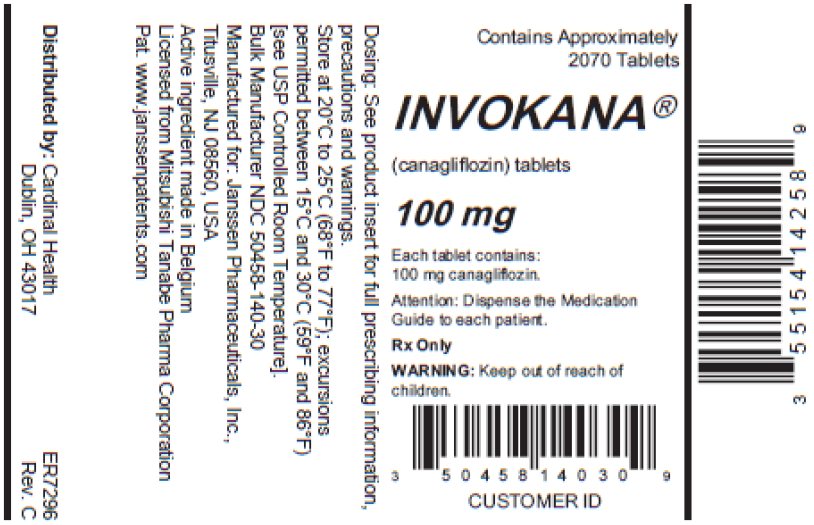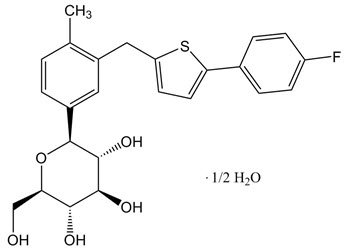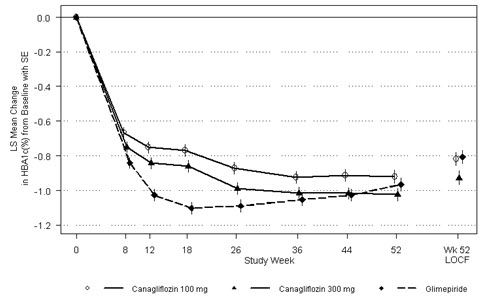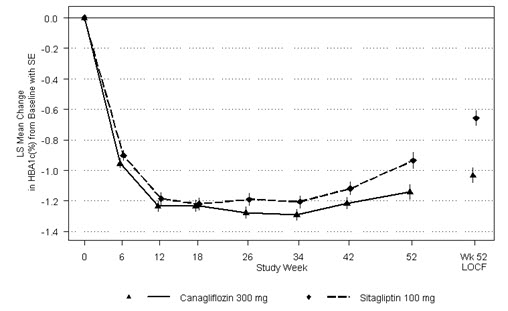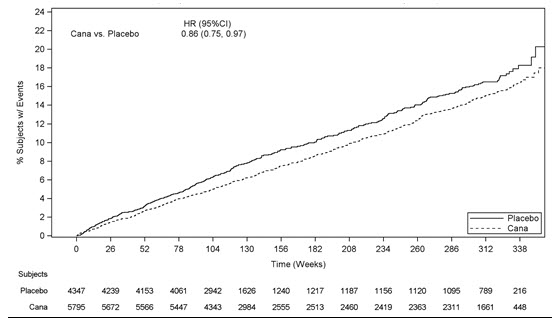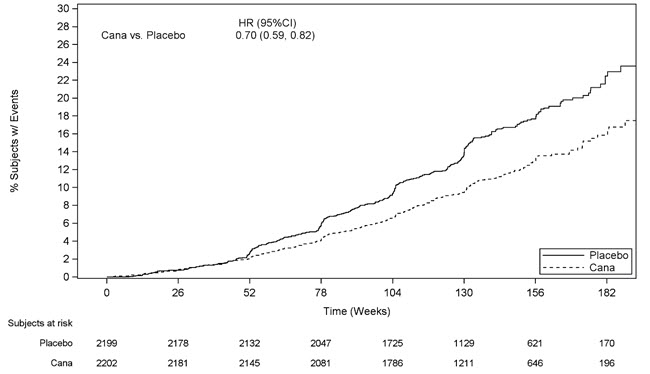 DRUG LABEL: INVOKANA
NDC: 55154-1425 | Form: TABLET, FILM COATED
Manufacturer: Cardinal Health 107, LLC
Category: prescription | Type: HUMAN PRESCRIPTION DRUG LABEL
Date: 20260217

ACTIVE INGREDIENTS: CANAGLIFLOZIN 100 mg/1 1
INACTIVE INGREDIENTS: CROSCARMELLOSE SODIUM; HYDROXYPROPYL CELLULOSE (1600000 WAMW); ANHYDROUS LACTOSE; MAGNESIUM STEARATE; MICROCRYSTALLINE CELLULOSE; FERRIC OXIDE YELLOW; POLYETHYLENE GLYCOL 3350; POLYVINYL ALCOHOL, UNSPECIFIED; TALC; TITANIUM DIOXIDE

HIGHLIGHTS OF PRESCRIBING INFORMATION

These highlights do not include all the information needed to use INVOKANA safely and effectively. See full prescribing information for INVOKANA.
INVOKANA ®(canagliflozin) tablets, for oral use
Initial U.S. Approval: 2013

RECENT MAJOR CHANGES

Indications and Usage (1) | 12/2024
Dosage and Administration (2.2, 2.3) | 12/2024
Dosage and Administration (2.5) | 08/2024
Warnings and Precautions (5.1) | 08/2024
Warnings and Precautions (5.2) | 08/2024

1 INDICATIONS AND USAGE

INVOKANA is a sodium-glucose co-transporter 2 (SGLT2) inhibitor indicated:

- As an adjunct to diet and exercise to improve glycemic control in adults and pediatric patients aged 10 years and older with type 2 diabetes mellitus (1).
- To reduce the risk of major adverse cardiovascular events in adults with type 2 diabetes mellitus and established cardiovascular disease (1).
- To reduce the risk of end-stage kidney disease, doubling of serum creatinine, cardiovascular death, and hospitalization for heart failure in adults with type 2 diabetes mellitus and diabetic nephropathy with albuminuria (1).

Limitations of Use:

- Not recommended for use to improve glycemic control in patients with type 1 diabetes mellitus (1).
- Not recommended for use to improve glycemic control in patients with type 2 diabetes mellitus with an eGFR less than 30 mL/min/1.73 m ^2(1).

2 DOSAGE AND ADMINISTRATION

- Assess renal function before initiating and as clinically indicated. Assess volume status and correct volume depletion before initiating (2.1).
- The recommended starting dosage in adults and pediatric patients aged 10 years and older with type 2 diabetes mellitus is 100 mg orally once daily, taken before the first meal of the day to improve glycemic control. The dosage can be increased to 300 mg once daily in patients tolerating 100 mg once daily who have an eGFR of 60 mL/min/1.73 m ^2or greater and require additional glycemic control (2.2).
- For all other indications in adults, the recommended dosage of INVOKANA is 100 mg orally once daily (2.2).
- Dosage adjustments for patients with renal impairment may be required (2.3).
- See full prescribing information for INVOKANA dosage modifications due to drug interactions (2.4).
- Withhold INVOKANA at least 3 days, if possible, prior to surgery or procedures associated with prolonged fasting (2.5).

3 DOSAGE FORMS AND STRENGTHS

Tablets: 100 mg, 300 mg (3)

4 CONTRAINDICATIONS

- Serious hypersensitivity reaction to INVOKANA (4)

5 WARNINGS AND PRECAUTIONS

- Diabetic Ketoacidosis in Patients with Type 1 Diabetes Mellitus and Other Ketoacidosis: Consider ketone monitoring in patients at risk for ketoacidosis, as indicated. Assess for ketoacidosis regardless of presenting blood glucose levels and discontinue INVOKANA if ketoacidosis is suspected. Monitor patients for resolution of ketoacidosis before restarting (5.1).
- Lower Limb Amputation: Monitor patients for infection or ulcers of lower limb and discontinue if these occur (5.2).
- Volume Depletion: May result in acute kidney injury. Before initiating INVOKANA, assess and correct volume status in patients with renal impairment, elderly patients, or patients on loop diuretics. Monitor for signs and symptoms during therapy (5.3).
- Urosepsis and Pyelonephritis: Evaluate patients for signs and symptoms of urinary tract infections and treat promptly, if indicated (5.4).
- Hypoglycemia with Concomitant Use with Insulin or Insulin Secretagogues: Consider a lower dose of insulin or the insulin secretagogue to reduce the risk of hypoglycemia when used in combination with INVOKANA (5.5).
- Necrotizing Fasciitis of the Perineum (Fournier's Gangrene): Serious, life-threatening cases have occurred in both females and males. Assess patients presenting with pain or tenderness, erythema, or swelling in the genital or perineal area, along with fever or malaise. If suspected, institute prompt treatment (5.6).
- Genital Mycotic Infections: Monitor and treat if indicated (5.7).
- Hypersensitivity Reactions: Discontinue INVOKANA and monitor until signs and symptoms resolve (5.8).
- Bone Fracture: Consider factors that contribute to fracture risk before initiating INVOKANA (5.9).

6 ADVERSE REACTIONS

Most common adverse reactions (5% or greater incidence): female genital mycotic infections, urinary tract infection, and increased urination (6.1).

To report SUSPECTED ADVERSE REACTIONS, contact Janssen Pharmaceuticals, Inc. at 1-800-526-7736 or FDA at 1-800-FDA-1088 or www.fda.gov/medwatch.

7 DRUG INTERACTIONS

See full prescribing information for information on drug interactions and interference of INVOKANA with laboratory tests (7).

8 USE IN SPECIFIC POPULATIONS

- Pregnancy: Advise females of the potential risk to a fetus especially during the second and third trimesters (8.1).
- Lactation: Not recommended when breastfeeding (8.2).
- Geriatrics: Higher incidence of adverse reactions related to reduced intravascular volume (8.5).
- Renal Impairment: Higher incidence of adverse reactions related to hypotension and renal function (8.6).
- Hepatic Impairment: Not recommended in patients with severe hepatic impairment (8.7).

FULL PRESCRIBING INFORMATION

1 INDICATIONS AND USAGE

INVOKANA (canagliflozin) is indicated:

- as an adjunct to diet and exercise to improve glycemic control in adults and pediatric patients aged 10 years and older with type 2 diabetes mellitus.
- to reduce the risk of major adverse cardiovascular events (cardiovascular death, nonfatal myocardial infarction and nonfatal stroke) in adults with type 2 diabetes mellitus and established cardiovascular disease (CVD).
- to reduce the risk of end-stage kidney disease (ESKD), doubling of serum creatinine, cardiovascular (CV) death, and hospitalization for heart failure in adults with type 2 diabetes mellitus and diabetic nephropathy with albuminuria greater than 300 mg/day.

Limitations of Use

INVOKANA is not recommended for use to improve glycemic control in patients with type 1 diabetes mellitus [see Warnings and Precautions (5.1)].

INVOKANA is not recommended for use to improve glycemic control in patients with type 2 diabetes mellitus with an eGFR less than 30 mL/min/1.73 m ^2. INVOKANA is likely to be ineffective in this setting based upon its mechanism of action.

2 DOSAGE AND ADMINISTRATION

2.1 Prior to Initiation of INVOKANA

Assess renal function before initiating INVOKANA and as clinically indicated [see Dosage and Administration (2.3)and Warnings and Precautions (5.3)].

In patients with volume depletion, correct this condition before initiating INVOKANA [see Warnings and Precautions (5.3)and Use in Specific Populations (8.5, 8.6)].

2.2 Recommended Dosage and Administration

Recommended Dosage for Glycemic Control in Adults and Pediatric Patients Aged 10 Years and Older

- The recommended starting dosage of INVOKANA is 100 mg orally once daily to improve glycemic control, taken before the first meal of the day.
- For additional glycemic control, the dosage of INVOKANA may be increased to the maximum recommended dosage of 300 mg once daily.

Recommended Dosage for Other Indications in Adults

The recommended dosage of INVOKANA is 100 mg orally once daily for the following indications in adults:

- to reduce the risk of major adverse cardiovascular events (cardiovascular death, nonfatal myocardial infarction and nonfatal stroke) in adults with type 2 diabetes mellitus and established cardiovascular disease (CVD).
- to reduce the risk of end-stage kidney disease (ESKD), doubling of serum creatinine, cardiovascular (CV) death, and hospitalization for heart failure in adults with type 2 diabetes mellitus and diabetic nephropathy with albuminuria greater than 300 mg/day.

2.3 Recommended Dosage in Adults and Pediatric Patients Aged 10 Years and Older with Renal Impairment

Table 1 provides dosage recommendations for adults and pediatric patients aged 10 years and older with renal impairment, based on estimated glomerular filtration rate (eGFR).

Table 1: Recommended Dosage in Adults and Pediatric Patients Aged 10 Years and Older with Renal Impairment
Estimated Glomerular Filtration Rate [eGFR (mL/min/1.73 m ^2)] | Recommended Dosage
eGFR 30 to less than 60 | The maximum recommended dosage is 100 mg orally once daily.
eGFR less than 30 | - Initiation is not recommended - Adult patients taking INVOKANA with albuminuria greater than 300 mg/day may continue INVOKANA 100 mg once daily to reduce the risk of ESKD, doubling of serum creatinine, CV death, and hospitalization for heart failure [see Indications and Usage (1)and Use in Specific Populations (8.6)].

2.4 Concomitant Use with UDP-Glucuronosyl transferase (UGT) Enzyme Inducers

When co-administering INVOKANA with an inducer of UGT (e.g., rifampin, phenytoin, phenobarbital, ritonavir), increase the dosage of INVOKANA based on renal function [see Drug Interactions (7)]:

- In patients with eGFR 60 mL/min/1.73 m ^2or greater, increase the dosage to 200 mg orally once daily in patients currently tolerating INVOKANA 100 mg once daily. The maximum recommended dosage of INVOKANA is 300 mg once daily.
- In patients with eGFR less than 60 mL/min/1.73 m ^2, increase to a maximum recommended dosage of 200 mg orally once daily in patients currently tolerating INVOKANA 100 mg once daily.

2.5 Temporary Interruption for Surgery

Withhold INVOKANA at least 3 days, if possible, prior to surgery or procedures associated with prolonged fasting. Resume INVOKANA when the patient is clinically stable and has resumed oral intake [see Warnings and Precautions (5.1) and Clinical Pharmacology (12.2)].

3 DOSAGE FORMS AND STRENGTHS

- INVOKANA 100 mg tablets are yellow, capsule-shaped, tablets with "CFZ" on one side and "100" on the other side.
- INVOKANA 300 mg tablets are white, capsule-shaped, tablets with "CFZ" on one side and "300" on the other side.

4 CONTRAINDICATIONS

INVOKANA is contraindicated in patients with a serious hypersensitivity reaction to INVOKANA, such as anaphylaxis or angioedema [see Warnings and Precautions (5.8)and Adverse Reactions (6.1, 6.2)].

5 WARNINGS AND PRECAUTIONS

5.1 Diabetic Ketoacidosis in Patients with Type 1 Diabetes Mellitus and Other Ketoacidosis

In patients with type 1 diabetes mellitus, INVOKANA significantly increases the risk of diabetic ketoacidosis, a life-threatening event, beyond the background rate. In placebo-controlled trials of patients with type 1 diabetes mellitus, the risk of ketoacidosis was markedly increased in patients who received sodium glucose transporter 2 (SGLT2) inhibitors compared to patients who received placebo; this risk may be greater with higher doses of INVOKANA. INVOKANA is not indicated for glycemic control in patients with type 1 diabetes mellitus.

Type 2 diabetes mellitus and pancreatic disorders (e.g., history of pancreatitis or pancreatic surgery) are also risk factors for ketoacidosis. There have been postmarketing reports of fatal events of ketoacidosis in patients with type 2 diabetes mellitus using SGLT2 inhibitors, including INVOKANA.

Precipitating conditions for diabetic ketoacidosis or other ketoacidosis include under-insulinization due to insulin dose reduction or missed insulin doses, acute febrile illness, reduced caloric intake, ketogenic diet, surgery, volume depletion, and alcohol abuse.

Signs and symptoms are consistent with dehydration and severe metabolic acidosis and include nausea, vomiting, abdominal pain, generalized malaise, and shortness of breath. Blood glucose levels at presentation may be below those typically expected for diabetic ketoacidosis (e.g., less than 250 mg/dL). Ketoacidosis and glucosuria may persist longer than typically expected.

Urinary glucose excretion persists for 3 days after discontinuing INVOKANA [see Clinical Pharmacology (12.2)]; however, there have been postmarketing reports of ketoacidosis and/or glucosuria lasting greater than 6 days and some up to 2 weeks after discontinuation of SGLT2 inhibitors.

Consider ketone monitoring in patients at risk for ketoacidosis if indicated by the clinical situation. Assess for ketoacidosis regardless of presenting blood glucose levels in patients who present with signs and symptoms consistent with severe metabolic acidosis. If ketoacidosis is suspected, discontinue INVOKANA, promptly evaluate, and treat ketoacidosis, if confirmed. Monitor patients for resolution of ketoacidosis before restarting INVOKANA.

Withhold INVOKANA, if possible, in temporary clinical situations that could predispose patients to ketoacidosis. Resume INVOKANA when the patient is clinically stable and has resumed oral intake [see Dosage and Administration (2.5)].

Educate all patients on the signs and symptoms of ketoacidosis and instruct patients to discontinue INVOKANA and seek medical attention immediately if signs and symptoms occur.

5.2 Lower Limb Amputation

An increased risk of lower limb amputations associated with INVOKANA use versus placebo was observed in CANVAS (5.9 vs 2.8 events per 1,000 patient-years) and CANVAS-R (7.5 vs 4.2 events per 1,000 patient-years), two randomized, placebo-controlled trials evaluating adult patients with type 2 diabetes mellitus who had either established cardiovascular disease or were at risk for cardiovascular disease. The risk of lower limb amputations was observed at both the 100 mg and 300 mg once daily dosage regimens. The amputation data for CANVAS and CANVAS-R are shown in Tables 3 and 4, respectively [see Adverse Reactions (6.1)].

Amputations of the toe and midfoot (99 out of 140 patients with amputations receiving INVOKANA in the two trials) were the most frequent; however, amputations involving the leg, below and above the knee, were also observed (41 out of 140 patients with amputations receiving INVOKANA in the two trials). Some patients had multiple amputations, some involving both lower limbs.

Lower limb infections, gangrene, and diabetic foot ulcers were the most common precipitating medical events leading to the need for an amputation. The risk of amputation was highest in patients with a baseline history of prior amputation, peripheral vascular disease, and neuropathy.

Counsel patients about the importance of routine preventative foot care. Monitor patients receiving INVOKANA for signs and symptoms of infection (including osteomyelitis), new pain or tenderness, sores or ulcers involving the lower limbs, and discontinue INVOKANA if these complications occur.

5.3 Volume Depletion

INVOKANA can cause intravascular volume contraction which may sometimes manifest as symptomatic hypotension or acute transient changes in creatinine [see Adverse Reactions (6.1)]. There have been post-marketing reports of acute kidney injury which are likely related to volume depletion, some requiring hospitalizations and dialysis, in patients with type 2 diabetes mellitus receiving SGLT2 inhibitors, including INVOKANA. Patients with impaired renal function (eGFR less than 60 mL/min/1.73 m ^2), elderly patients, or patients on loop diuretics may be at increased risk for volume depletion or hypotension. Before initiating INVOKANA in patients with one or more of these characteristics, assess and correct volume status. Monitor for signs and symptoms of volume depletion after initiating therapy.

5.4 Urosepsis and Pyelonephritis

There have been postmarketing reports of serious urinary tract infections including urosepsis and pyelonephritis requiring hospitalization in patients receiving INVOKANA. Treatment with INVOKANA increases the risk for urinary tract infections. Evaluate patients for signs and symptoms of urinary tract infections and treat promptly, if indicated [see Adverse Reactions (6)].

5.5 Hypoglycemia with Concomitant Use with Insulin or Insulin Secretagogues

Insulin and insulin secretagogues are known to cause hypoglycemia. INVOKANA may increase the risk of hypoglycemia when combined with insulin or an insulin secretagogue [see Adverse Reactions (6.1)]. The risk of hypoglycemia may be lowered by a reduction in the dose of sulfonylurea (or other concomitantly administered insulin secretagogues) or insulin. Inform patients using these concomitant medications of the risk of hypoglycemia and educate them on the signs and symptoms of hypoglycemia.

5.6 Necrotizing Fasciitis of the Perineum (Fournier's Gangrene)

Reports of necrotizing fasciitis of the perineum (Fournier's gangrene), a rare but serious and life-threatening necrotizing infection requiring urgent surgical intervention, have been identified in postmarketing surveillance in patients with diabetes mellitus receiving SGLT2 inhibitors, including INVOKANA. Cases have been reported in both females and males. Serious outcomes have included hospitalization, multiple surgeries, and death.

Patients treated with INVOKANA presenting with pain or tenderness, erythema, or swelling in the genital or perineal area, along with fever or malaise, should be assessed for necrotizing fasciitis. If suspected, start treatment immediately with broad-spectrum antibiotics and, if necessary, surgical debridement. Discontinue INVOKANA, closely monitor blood glucose levels, and provide appropriate alternative therapy for glycemic control.

5.7 Genital Mycotic Infections

INVOKANA increases the risk of genital mycotic infections. Patients with a history of genital mycotic infections and uncircumcised males were more likely to develop genital mycotic infections [see Adverse Reactions (6.1)]. Monitor and treat appropriately.

5.8 Hypersensitivity Reactions

Hypersensitivity reactions, including angioedema and anaphylaxis, have been reported with INVOKANA. These reactions generally occurred within hours to days after initiating INVOKANA. If hypersensitivity reactions occur, discontinue use of INVOKANA; treat and monitor until signs and symptoms resolve [see Contraindications (4)and Adverse Reactions (6.1, 6.2)].

5.9 Bone Fracture

An increased risk of bone fracture, occurring as early as 12 weeks after treatment initiation, was observed in adult patients using INVOKANA in the CANVAS trial [see Clinical Studies (14.3)]. Consider factors that contribute to fracture risk prior to initiating INVOKANA [see Adverse Reactions (6.1)].

6 ADVERSE REACTIONS

The following important adverse reactions are described below and elsewhere in the labeling:

- Diabetic Ketoacidosis in Patients with Type 1 Diabetes and Other Ketoacidosis [see Warnings and Precautions (5.1)]
- Lower Limb Amputation [see Warnings and Precautions (5.2)]
- Volume Depletion [see Warnings and Precautions (5.3)]
- Urosepsis and Pyelonephritis [see Warnings and Precautions (5.4)]
- Hypoglycemia with Concomitant Use with Insulin or Insulin Secretagogues [see Warnings and Precautions (5.5)]
- Necrotizing Fasciitis of the Perineum (Fournier's gangrene) [see Warnings and Precautions (5.6)]
- Genital Mycotic Infections [see Warnings and Precautions (5.7)]
- Hypersensitivity Reactions [see Warnings and Precautions (5.8)]
- Bone Fracture [see Warnings and Precautions (5.9)]

6.1 Clinical Studies Experience

Because clinical trials are conducted under widely varying conditions, adverse reaction rates observed in the clinical trials of a drug cannot be directly compared to the rates in the clinical trials of another drug and may not reflect the rates observed in clinical practice.

INVOKANA has been evaluated in clinical trials in adults and pediatric patients aged 10 years and older with type 2 diabetes mellitus. Additionally, INVOKANA has been studied in clinical trials in adult patients with type 2 diabetes mellitus who also have heart failure or chronic kidney disease. The overall safety profile of INVOKANA was consistent across the studied indications.

Clinical Trials in Adult Patients with Type 2 Diabetes Mellitus

Pool of Placebo-Controlled Trials for Glycemic Control

The data in Table 2 are derived from four 26-week placebo-controlled trials where INVOKANA was used as monotherapy in one trial and as add-on therapy in three trials. These data reflect exposure of 1,667 adult patients to INVOKANA and a mean duration of exposure to INVOKANA of 24 weeks. Patients received INVOKANA 100 mg (N=833), INVOKANA 300 mg (N=834) or placebo (N=646) once daily. The mean age of the population was 56 years and 2% were older than 75 years of age. Fifty percent (50%) of the population was male and 72% were White, 12% were Asian, and 5% were Black or African American. At baseline the population had diabetes for an average of 7.3 years, had a mean HbA 1Cof 8.0% and 20% had established microvascular complications of diabetes. Baseline renal function was normal or mildly impaired (mean eGFR 88 mL/min/1.73 m ^2).

Table 2 shows common adverse reactions associated with the use of INVOKANA. These adverse reactions were not present at baseline, occurred more commonly on INVOKANA than on placebo, and occurred in at least 2% of patients treated with either INVOKANA 100 mg or INVOKANA 300 mg.

Table 2: Adverse Reactions from Pool of Four 26–Week Placebo-Controlled Trials Reported in ≥ 2% of INVOKANA-Treated Adult Patients [The four placebo-controlled trials included one monotherapy trial and three add-on combination trials with metformin HCl, metformin HCl and sulfonylurea, or metformin HCl and pioglitazone.]
Adverse Reaction | Placebo N=646 | INVOKANA 100 mg N=833 | INVOKANA 300 mg N=834
Urinary tract infections [Urinary tract infections include the following adverse reactions: Urinary tract infection, Cystitis, Kidney infection, and Urosepsis.] | 3.8% | 5.9% | 4.4%
Increased urination [Increased urination includes the following adverse reactions: Polyuria, Pollakiuria, Urine output increased, Micturition urgency, and Nocturia.] | 0.7% | 5.1% | 4.6%
Thirst [Thirst includes the following adverse reactions: Thirst, Dry mouth, and Polydipsia.] | 0.1% | 2.8% | 2.4%
Constipation | 0.9% | 1.8% | 2.4%
Nausea | 1.6% | 2.1% | 2.3%
 | N=312 | N=425 | N=430
Female genital mycotic infections [Female genital mycotic infections include the following adverse reactions: Vulvovaginal candidiasis, Vulvovaginal mycotic infection, Vulvovaginitis, Vaginal infection, Vulvitis, and Genital infection fungal.] | 2.8% | 10.6% | 11.6%
Vulvovaginal pruritus | 0.0% | 1.6% | 3.2%
 | N=334 | N=408 | N=404
Male genital mycotic infections [Male genital mycotic infections include the following adverse reactions: Balanitis or Balanoposthitis, Balanitis candida, and Genital infection fungal.] | 0.7% | 4.2% | 3.8%
Note: Percentages were weighted by studies. Trial weights were proportional to the harmonic mean of the three treatment sample sizes.

Abdominal pain was also more commonly reported in patients taking INVOKANA 100 mg (1.8%), 300 mg (1.7%) than in patients taking placebo (0.8%).

Placebo-Controlled Trial in Diabetic Nephropathy

The occurrence of adverse reactions for INVOKANA was evaluated in patients participating in CREDENCE, a trial in adult patients with type 2 diabetes mellitus and diabetic nephropathy with albuminuria > 300 mg/day [see Clinical Studies (14.4)]. These data reflect exposure of 2,201 adult patients to INVOKANA and a mean duration of exposure to INVOKANA of 137 weeks.

- The rate of lower limb amputations associated with the use of INVOKANA 100 mg relative to placebo was 12.3 vs 11.2 events per 1,000 patient-years, respectively, with 2.6 years mean duration of follow-up.
- The incidence of hypotension was 2.8% and 1.5% on INVOKANA 100 mg and placebo, respectively.

Pool of Placebo- and Active-Controlled Trials for Glycemic Control and Cardiovascular Outcomes in Adult Patients

The occurrence of adverse reactions for INVOKANA was evaluated in adult patients participating in placebo- and active-controlled trials and in an integrated analysis of two cardiovascular trials, CANVAS and CANVAS-R.

The types and frequency of common adverse reactions observed in the pool of eight clinical trials (which reflect an exposure of 6,177 adult patients to INVOKANA) were consistent with those listed in Table 2. Percentages were weighted by trials. Trial weights were proportional to the harmonic mean of the three treatment sample sizes. In this pool, INVOKANA was also associated with the adverse reactions of fatigue (1.8%, 2.2%, and 2.0% with comparator, INVOKANA 100 mg, and INVOKANA 300 mg, respectively) and loss of strength or energy (i.e., asthenia) (0.6%, 0.7%, and 1.1% with comparator, INVOKANA 100 mg, and INVOKANA 300 mg, respectively).

In the pool of eight clinical trials, the incidence rate of pancreatitis (acute or chronic) was 0.1%, 0.2%, and 0.1% receiving comparator, INVOKANA 100 mg, and INVOKANA 300 mg, respectively.

In the pool of eight clinical trials, hypersensitivity-related adverse reactions (including erythema, rash, pruritus, urticaria, and angioedema) occurred in 3.0%, 3.8%, and 4.2% of adult patients receiving comparator, INVOKANA 100 mg, and INVOKANA 300 mg, respectively. Five patients experienced serious adverse reactions of hypersensitivity with INVOKANA, which included 4 patients with urticaria and 1 patient with a diffuse rash and urticaria occurring within hours of exposure to INVOKANA. Among these patients, 2 patients discontinued INVOKANA. One patient with urticaria had recurrence when INVOKANA was re-initiated.

Photosensitivity-related adverse reactions (including photosensitivity reaction, polymorphic light eruption, and sunburn) occurred in 0.1%, 0.2%, and 0.2% of patients receiving comparator, INVOKANA 100 mg, and INVOKANA 300 mg, respectively.

Other adverse reactions occurring more frequently on INVOKANA than on comparator were:

Lower Limb Amputation

An increased risk of lower limb amputations associated with INVOKANA use versus placebo was observed in CANVAS (5.9 vs 2.8 events per 1,000 patient-years) and CANVAS-R (7.5 vs 4.2 events per 1,000 patient-years), two randomized, placebo-controlled trials evaluating adult patients with type 2 diabetes who had either established cardiovascular disease or were at risk for cardiovascular disease. Patients in CANVAS and CANVAS-R were followed for an average of 5.7 and 2.1 years, respectively [see Clinical Studies (14.3)]. The amputation data for CANVAS and CANVAS-R are shown in Tables 3 and 4, respectively.

Table 3: Amputations in the CANVAS Trial in Adults with Type 2 Diabetes Mellitus and Atherosclerotic Cardiovascular Disease
 | Placebo N=1,441 | INVOKANA 100 mg N=1,445 | INVOKANA 300 mg N=1,441 | INVOKANA (Pooled) N=2,886
Patients with an amputation, n (%) | 22 (1.5) | 50 (3.5) | 45 (3.1) | 95 (3.3)
Total amputations | 33 | 83 | 79 | 162
Amputation incidence rate (per 1,000 patient-years) | 2.8 | 6.2 | 5.5 | 5.9
Hazard Ratio (95% CI) | -- | 2.24 (1.36, 3.69) | 2.01 (1.20, 3.34) | 2.12 (1.34, 3.38)
Note: Incidence is based on the number of patients with at least one amputation, and not the total number of amputation events. A patient's follow-up is calculated from Day 1 to the first amputation event date. Some patients had more than one amputation.

Table 4: Amputations in the CANVAS-R Trial in Adults with Type 2 Diabetes Mellitus and Atherosclerotic Cardiovascular Disease
 | Placebo N=2,903 | INVOKANA 100 mg (with up-titration to 300 mg) N=2,904
Patients with an amputation, n (%) | 25 (0.9) | 45 (1.5)
Total amputations | 36 | 59
Amputation incidence rate (per 1,000 patient-years) | 4.2 | 7.5
Hazard Ratio (95% CI) | -- | 1.80 (1.10, 2.93)
Note: Incidence is based on the number of patients with at least one amputation, and not the total number of amputation events. A patient's follow-up is calculated from Day 1 to the first amputation event date. Some patients had more than one amputation.

Renal Cell Carcinoma

In the CANVAS trial in adults (mean duration of follow-up of 5.7 years) [see Clinical Studies (14.3)], the incidence of renal cell carcinoma was 0.15% (2/1,331) and 0.29% (8/2,716) for placebo and INVOKANA, respectively, excluding patients with less than 6 months of follow-up, less than 90 days of treatment, or a history of renal cell carcinoma. A causal relationship to INVOKANA could not be established due to the limited number of cases.

Volume Depletion-Related Adverse Reactions

INVOKANA results in an osmotic diuresis, which may lead to reductions in intravascular volume. In clinical trials for glycemic control, treatment with INVOKANA was associated with a dose-dependent increase in the incidence of volume depletion-related adverse reactions (e.g., hypotension, postural dizziness, orthostatic hypotension, syncope, and dehydration). An increased incidence was observed in adult patients on the 300 mg dose. The three factors associated with the largest increase in volume depletion-related adverse reactions in these trials were the use of loop diuretics, moderate renal impairment (eGFR 30 to less than 60 mL/min/1.73 m ^2), and age 75 years and older (Table 5) [see Use in Specific Populations (8.5and 8.6)].

Table 5: Proportion of Adult Patients with at Least One Volume Depletion-Related Adverse Reaction (Pooled Results from 8 Clinical Trials for Glycemic Control)
Baseline Characteristic | Comparator Group [Includes placebo and active-comparator groups] % | INVOKANA 100 mg % | INVOKANA 300 mg %
Overall population | 1.5% | 2.3% | 3.4%
75 years of age and older [Patients could have more than 1 of the listed risk factors] | 2.6% | 4.9% | 8.7%
eGFR less than 60 mL/min/1.73 m ^2 | 2.5% | 4.7% | 8.1%
Use of loop diuretic | 4.7% | 3.2% | 8.8%

Falls

In a pool of nine clinical trials in adults with mean duration of exposure to INVOKANA of 85 weeks, the proportion of patients who experienced falls was 1.3%, 1.5%, and 2.1% with comparator, INVOKANA 100 mg, and INVOKANA 300 mg, respectively. The higher risk of falls for patients treated with INVOKANA was observed within the first few weeks of treatment.

Genital Mycotic Infections

In the pool of four placebo-controlled clinical trials in adults for glycemic control, female genital mycotic infections (e.g., vulvovaginal mycotic infection, vulvovaginal candidiasis, and vulvovaginitis) occurred in 2.8%, 10.6%, and 11.6% of females treated with placebo, INVOKANA 100 mg, and INVOKANA 300 mg, respectively. Patients with a history of genital mycotic infections were more likely to develop genital mycotic infections on INVOKANA. Female patients who developed genital mycotic infections on INVOKANA were more likely to experience recurrence and require treatment with oral or topical antifungal agents and anti-microbial agents. In females, discontinuation due to genital mycotic infections occurred in 0% and 0.7% of patients treated with placebo and INVOKANA, respectively.

In the pool of four placebo-controlled clinical trials in adults, male genital mycotic infections (e.g., candidal balanitis, balanoposthitis) occurred in 0.7%, 4.2%, and 3.8% of males treated with placebo, INVOKANA 100 mg, and INVOKANA 300 mg, respectively. Male genital mycotic infections occurred more commonly in uncircumcised males and in males with a prior history of balanitis or balanoposthitis. Male patients who developed genital mycotic infections on INVOKANA were more likely to experience recurrent infections (22% on INVOKANA versus none on placebo) and require treatment with oral or topical antifungal agents and anti-microbial agents than patients on comparators. In males, discontinuations due to genital mycotic infections occurred in 0% and 0.5% of patients treated with placebo and INVOKANA, respectively.

In the pooled analysis of 8 randomized trials in adults evaluating glycemic control, phimosis was reported in 0.3% of uncircumcised male patients treated with INVOKANA and 0.2% required circumcision to treat the phimosis.

Hypoglycemia

In all glycemic control trials, hypoglycemia was defined as any event regardless of symptoms, where biochemical hypoglycemia was documented (any glucose value below or equal to 70 mg/dL). Severe hypoglycemia was defined as an event consistent with hypoglycemia where the patient required the assistance of another person to recover, lost consciousness, or experienced a seizure (regardless of whether biochemical documentation of a low glucose value was obtained). In individual clinical trials of glycemic control in adults [see Clinical Studies (14.1)], episodes of hypoglycemia occurred at a higher rate when INVOKANA was co-administered with insulin or sulfonylureas (Table 6).

Table 6: Incidence of Hypoglycemia [Number of patients experiencing at least one event of hypoglycemia based on either biochemically documented episodes or severe hypoglycemic events in the intent-to-treat population] in Randomized Clinical Trials of Glycemic Control in Adults
Monotherapy (26 weeks) | Placebo (N=192) | INVOKANA 100 mg (N=195) | INVOKANA 300 mg (N=197)
Overall [N (%)] | 5 (2.6) | 7 (3.6) | 6 (3.0)
In Combination with Metformin HCl (26 weeks) | Placebo + Metformin HCl (N=183) | INVOKANA 100 mg + Metformin HCl (N=368) | INVOKANA 300 mg + Metformin HCl (N=367)
Overall [N (%)] | 3 (1.6) | 16 (4.3) | 17 (4.6)
Severe [N (%)] [Severe episodes of hypoglycemia were defined as those where the patient required the assistance of another person to recover, lost consciousness, or experienced a seizure (regardless of whether biochemical documentation of a low glucose value was obtained)] | 0 (0) | 1 (0.3) | 1 (0.3)
In Combination with Metformin HCl (52 weeks) | Glimepiride + Metformin HCl (N=482) | INVOKANA 100 mg + Metformin HCl (N=483) | INVOKANA 300 mg + Metformin HCl (N=485)
Overall [N (%)] | 165 (34.2) | 27 (5.6) | 24 (4.9)
Severe [N (%)] | 15 (3.1) | 2 (0.4) | 3 (0.6)
In Combination with Sulfonylurea (18 weeks) | Placebo + Sulfonylurea (N=69) | INVOKANA 100 mg + Sulfonylurea (N=74) | INVOKANA 300 mg + Sulfonylurea (N=72)
Overall [N (%)] | 4 (5.8) | 3 (4.1) | 9 (12.5)
In Combination with Metformin HCl + Sulfonylurea (26 weeks) | Placebo + Metformin HCl + Sulfonylurea (N=156) | INVOKANA 100 mg + Metformin HCl + Sulfonylurea (N=157) | INVOKANA 300 mg + Metformin HCl + Sulfonylurea (N=156)
Overall [N (%)] | 24 (15.4) | 43 (27.4) | 47 (30.1)
Severe [N (%)] | 1 (0.6) | 1 (0.6) | 0
In Combination with Metformin HCl + Sulfonylurea (52 weeks) | Sitagliptin + Metformin HCl + Sulfonylurea (N=378) |  | INVOKANA 300 mg + Metformin HCl + Sulfonylurea (N=377)
Overall [N (%)] | 154 (40.7) |  | 163 (43.2)
Severe [N (%)] | 13 (3.4) |  | 15 (4.0)
In Combination with Metformin HCl + Pioglitazone (26 weeks) | Placebo + Metformin HCl + Pioglitazone (N=115) | INVOKANA 100 mg + Metformin HCl + Pioglitazone (N=113) | INVOKANA 300 mg + Metformin HCl + Pioglitazone (N=114)
Overall [N (%)] | 3 (2.6) | 3 (2.7) | 6 (5.3)
In Combination with Insulin (18 weeks) | Placebo (N=565) | INVOKANA 100 mg (N=566) | INVOKANA 300 mg (N=587)
Overall [N (%)] | 208 (36.8) | 279 (49.3) | 285 (48.6)
Severe [N (%)] | 14 (2.5) | 10 (1.8) | 16 (2.7)

Bone Fracture

In the CANVAS trial in adults [see Clinical Studies (14.3)], the incidence rates of all adjudicated bone fracture were 1.09, 1.59, and 1.79 events per 100 patient-years of follow-up to placebo, INVOKANA 100 mg, and INVOKANA 300 mg, respectively. The fracture imbalance was observed within the first 26 weeks of therapy and remained through the end of the trial. Fractures were more likely to be low trauma (e.g., fall from no more than standing height), and affect the distal portion of upper and lower extremities.

Laboratory and Imaging Tests

Increases in Serum Creatinine and Decreases in eGFR

Initiation of INVOKANA causes an increase in serum creatinine and decrease in estimated GFR. In adult patients with moderate renal impairment, the increase in serum creatinine generally does not exceed 0.2 mg/dL, occurs within the first 6 weeks of starting therapy, and then stabilizes. Increases that do not fit this pattern should prompt further evaluation to exclude the possibility of acute kidney injury [see Clinical Pharmacology (12.1)]. The acute effect on eGFR reverses after treatment discontinuation suggesting acute hemodynamic changes may play a role in the renal function changes observed with INVOKANA.

Increases in Serum Potassium

In a pooled population of adult patients (N=723) in glycemic control trials with moderate renal impairment (eGFR 45 to less than 60 mL/min/1.73 m ^2), increases in serum potassium to greater than 5.4 mEq/L and 15% above baseline occurred in 5.3%, 5.0%, and 8.8% of patients treated with placebo, INVOKANA 100 mg, and INVOKANA 300 mg, respectively. Severe elevations (greater than or equal to 6.5 mEq/L) occurred in 0.4% of patients treated with placebo, no patients treated with INVOKANA 100 mg, and 1.3% of patients treated with INVOKANA 300 mg.

In these patients, increases in potassium were more commonly seen in those with elevated potassium at baseline. Among patients with moderate renal impairment, approximately 84% were taking medications that interfere with potassium excretion, such as potassium-sparing diuretics, angiotensin-converting-enzyme inhibitors, and angiotensin-receptor blockers [see Use in Specific Populations (8.6)].

In CREDENCE, no difference in serum potassium, no increase in adverse events of hyperkalemia, and no increase in absolute (> 6.5 mEq/L) or relative (> upper limit of normal and > 15% increase from baseline) increases in serum potassium were observed in adults treated with INVOKANA 100 mg relative to placebo.

Increases in Low-Density Lipoprotein Cholesterol (LDL-C) and non-High-Density Lipoprotein Cholesterol (non-HDL-C)

In the pool of four glycemic control placebo-controlled trials in adults, dose-related increases in LDL-C with INVOKANA were observed. Mean changes (percent changes) from baseline in LDL-C relative to placebo were 4.4 mg/dL (4.5%) and 8.2 mg/dL (8.0%) with INVOKANA 100 mg and INVOKANA 300 mg, respectively. The mean baseline LDL-C levels were 104 to 110 mg/dL across treatment groups.

Dose-related increases in non-HDL-C with INVOKANA were observed in adults. Mean changes (percent changes) from baseline in non-HDL-C relative to placebo were 2.1 mg/dL (1.5%) and 5.1 mg/dL (3.6%) with INVOKANA 100 mg and 300 mg, respectively. The mean baseline non-HDL-C levels were 140 to 147 mg/dL across treatment groups.

Increases in Hemoglobin

In the pool of four placebo-controlled trials of glycemic control in adults, mean changes (percent changes) from baseline in hemoglobin were -0.18 g/dL (-1.1%) with placebo, 0.47 g/dL (3.5%) with INVOKANA 100 mg, and 0.51 g/dL (3.8%) with INVOKANA 300 mg. The mean baseline hemoglobin value was approximately 14.1 g/dL across treatment groups. At the end of treatment, 0.8%, 4.0%, and 2.7% of patients treated with placebo, INVOKANA 100 mg, and INVOKANA 300 mg, respectively, had hemoglobin above the upper limit of normal.

Decreases in Bone Mineral Density

Bone mineral density (BMD) was measured by dual-energy X-ray absorptiometry in a clinical trial of 714 older adults (mean age 64 years) [see Clinical Studies (14.1)]. At 2 years, adult patients randomized to INVOKANA 100 mg and INVOKANA 300 mg had placebo-corrected declines in BMD at the total hip of 0.9% and 1.2%, respectively, and at the lumbar spine of 0.3% and 0.7%, respectively. Additionally, placebo-adjusted BMD declines were 0.1% at the femoral neck for both INVOKANA doses and 0.4% at the distal forearm for patients randomized to INVOKANA 300 mg. The placebo-adjusted change at the distal forearm for patients randomized to INVOKANA 100 mg was 0%.

Clinical Trial in Pediatric Patients Aged 10 Years and Older with Type 2 Diabetes Mellitus

INVOKANA was administered to 84 pediatric patients in a double-blind, placebo-controlled trial of 171 pediatric patients aged 10 to 17 years with a mean exposure to INVOKANA of 48.3 weeks [see Clinical Studies (14.2)]. At baseline, background therapies included metformin monotherapy (46%), metformin and insulin (29%), diet and exercise only (14%), and insulin monotherapy (11%). Approximately 42% were Asian, 42% were White, 11% were Black or African American, 5% were American Indian/Alaska Native, and 36% identified as Hispanic or Latino ethnicity. The mean baseline eGFR was 157.3 mL/min/1.73 m ^2, and approximately 16% (24/151) of the trial population with measurements had microalbuminuria or macroalbuminuria. The safety profile of pediatric patients treated with INVOKANA was similar to that observed in adults with type 2 diabetes mellitus.

6.2 Postmarketing Experience

Additional adverse reactions have been identified during post-approval use of INVOKANA. Because these reactions are reported voluntarily from a population of uncertain size, it is generally not possible to reliably estimate their frequency or establish a causal relationship to drug exposure.

Metabolism and Nutrition
Ketoacidosis

Renal and Urinary
Acute Kidney Injury

Immune System
Anaphylaxis

Skin and Subcutaneous Tissue
Angioedema

Infections
Urosepsis and Pyelonephritis, Necrotizing Fasciitis of the Perineum (Fournier's gangrene)

7 DRUG INTERACTIONS

Table 7: Clinically Significant Drug Interactions with INVOKANA
UGT Enzyme Inducers
Clinical Impact: | UGT enzyme inducers decrease canagliflozin exposure which may reduce the effectiveness of INVOKANA.
Intervention: | For patients with eGFR 60 mL/min/1.73 m ^2or greater, if an inducer of UGTs is administered with INVOKANA, increase the dosage to 200 mg daily in patients currently tolerating INVOKANA 100 mg daily. The total daily dosage may be increased to 300 mg daily in patients currently tolerating INVOKANA 200 mg daily who require additional glycemic control. For patients with eGFR less than 60 mL/min/1.73 m ^2, if an inducer of UGTs is administered with INVOKANA, increase the dosage to 200 mg daily in patients currently tolerating INVOKANA 100 mg daily. Consider adding another antihyperglycemic agent in patients who require additional glycemic control [see Dosage and Administration (2.3)and Clinical Pharmacology (12.3)].
Examples: | Rifampin, phenytoin, phenobarbital, ritonavir
Insulin or Insulin Secretagogues
Clinical Impact: | The risk of hypoglycemia is increased when INVOKANA is used concomitantly with insulin secretagogues (e.g., sulfonylurea) or insulin.
Intervention: | Concomitant use may require a lower dosage of the insulin secretagogue or insulin to reduce the risk of hypoglycemia.
Digoxin
Clinical Impact: | Canagliflozin increases digoxin exposure [see Clinical Pharmacology (12.3)].
Intervention: | Monitor patients taking INVOKANA with concomitant digoxin for a need to adjust the dosage of digoxin.
Lithium
Clinical Impact: | Concomitant use of an SGLT2 inhibitor with lithium may decrease serum lithium concentrations.
Intervention: | Monitor serum lithium concentration more frequently during INVOKANA initiation and dosage changes.
Drug/Laboratory Test Interference
Positive Urine Glucose Test
Clinical Impact: | SGLT2 inhibitors increase urinary glucose excretion which will lead to positive urine glucose tests.
Intervention: | Monitoring glycemic control with urine glucose tests is not recommended in patients taking SGLT2 inhibitors. Use alternative methods to monitor glycemic control.
Interference with 1,5-anhydroglucitol (1,5-AG) Assay
Clinical Impact: | Measurements of 1,5-AG are unreliable in assessing glycemic control in patients taking SGLT2 inhibitors.
Intervention: | Monitoring glycemic control with 1,5-AG assay is not recommended in patients taking SGLT2 inhibitors. Use alternative methods to monitor glycemic control.

8 USE IN SPECIFIC POPULATIONS

8.1 Pregnancy

Risk Summary

Based on juvenile animal data showing adverse renal effects, INVOKANA is not recommended during the second and third trimesters of pregnancy.

Limited data with INVOKANA in pregnant women are not sufficient to determine a drug-associated risk for major birth defects or miscarriage. There are risks to the mother and fetus associated with poorly controlled diabetes in pregnancy [see Clinical Considerations].

In juvenile animal studies, adverse renal pelvic and tubule dilatations that were not reversible were observed in rats when canagliflozin was administered during a period of renal development corresponding to the late second and third trimesters of human pregnancy, at an exposure 0.5-times the 300 mg clinical dose, based on AUC.

The estimated background risk of major birth defects is 6–10% in women with pre-gestational diabetes with a HbA 1C>7 and has been reported to be as high as 20–25% in women with a HbA 1C>10. The estimated background risk of miscarriage for the indicated population is unknown. In the U.S. general population, the estimated background risk of major birth defects and miscarriage in clinically recognized pregnancies is 2–4% and 15–20%, respectively.

Clinical Considerations

Disease-Associated Maternal and/or Embryo/Fetal Risk

Poorly controlled diabetes in pregnancy increases the maternal risk for diabetic ketoacidosis, pre-eclampsia, spontaneous abortions, preterm delivery, and delivery complications. Poorly controlled diabetes increases the fetal risk for major birth defects, stillbirth, and macrosomia related morbidity.

Animal Data

Canagliflozin dosed directly to juvenile rats from postnatal day (PND) 21 until PND 90 at doses of 4, 20, 65, or 100 mg/kg increased kidney weights and dose dependently increased the incidence and severity of renal pelvic and tubular dilatation at all doses tested. Exposure at the lowest dose was greater than or equal to 0.5-times the 300 mg clinical dose, based on AUC. These outcomes occurred with drug exposure during periods of renal development in rats that correspond to the late second and third trimester of human renal development. The renal pelvic dilatations observed in juvenile animals did not fully reverse within a 1-month recovery period.

In embryo-fetal development studies in rats and rabbits, canagliflozin was administered for intervals coinciding with the first trimester period of organogenesis in humans. No developmental toxicities independent of maternal toxicity were observed when canagliflozin was administered at doses up to 100 mg/kg in pregnant rats and 160 mg/kg in pregnant rabbits during embryonic organogenesis or during a study in which maternal rats were dosed from gestation day (GD) 6 through PND 21, yielding exposures up to approximately 19-times the 300 mg clinical dose, based on AUC.

8.2 Lactation

Risk Summary

There is no information regarding the presence of INVOKANA in human milk, the effects on the breastfed infant, or the effects on milk production. Canagliflozin is present in the milk of lactating rats [see Data]. Since human kidney maturation occurs in utero and during the first 2 years of life when lactational exposure may occur, there may be risk to the developing human kidney.

Because of the potential for serious adverse reactions in a breastfed infant, advise women that use of INVOKANA is not recommended while breastfeeding.

Data

Animal Data

Radiolabeled canagliflozin administered to lactating rats on day 13 post-partum was present at a milk/plasma ratio of 1.40, indicating that canagliflozin and its metabolites are transferred into milk at a concentration comparable to that in plasma. Juvenile rats directly exposed to canagliflozin showed a risk to the developing kidney (renal pelvic and tubular dilatations) during maturation.

8.4 Pediatric Use

The safety and effectiveness of INVOKANA as an adjunct to diet and exercise to improve glycemic control in type 2 diabetes mellitus have been established in pediatric patients aged 10 years and older.

Use of INVOKANA for this indication is supported by evidence from a 52-week double-blind, placebo-controlled trial in 171 pediatric patients aged 10 to 17 years with type 2 diabetes mellitus and in a pediatric pharmacokinetic study [see Clinical Pharmacology (12.3)and Clinical Studies (14.2)]. The safety profile of pediatric patients treated with INVOKANA was similar to that observed in adults with type 2 diabetes mellitus.

The safety and effectiveness of INVOKANA for glycemic control in patients with type 2 diabetes have not been established in pediatric patients under 10 years of age.

The safety and effectiveness of INVOKANA have not been established in pediatric patients to reduce the risk of:

- major adverse cardiovascular events (cardiovascular death, nonfatal myocardial infarction and nonfatal stroke) in patients with type 2 diabetes mellitus and established cardiovascular disease (CVD).
- end-stage kidney disease (ESKD), doubling of serum creatinine, cardiovascular (CV) death, and hospitalization for heart failure in patients with type 2 diabetes mellitus and diabetic nephropathy with albuminuria greater than 300 mg/day.

8.5 Geriatric Use

In 13 clinical trials of INVOKANA, 2,294 patients 65 years and older, and 351 patients 75 years and older were exposed to INVOKANA [see Clinical Studies (14.1)].

Patients 65 years and older had a higher incidence of adverse reactions related to reduced intravascular volume with INVOKANA (such as hypotension, postural dizziness, orthostatic hypotension, syncope, and dehydration), particularly with the 300 mg daily dose, compared to younger patients; a more prominent increase in the incidence was seen in patients who were 75 years and older [see Dosage and Administration (2.1)and Adverse Reactions (6.1)]. Smaller reductions in HbA 1Cwith INVOKANA relative to placebo were seen in older (65 years and older; -0.61% with INVOKANA 100 mg and -0.74% with INVOKANA 300 mg relative to placebo) compared to younger patients (-0.72% with INVOKANA 100 mg and -0.87% with INVOKANA 300 mg relative to placebo).

8.6 Renal Impairment

The efficacy and safety of INVOKANA for glycemic control were evaluated in a trial that included adult patients with moderate renal impairment (eGFR 30 to less than 50 mL/min/1.73 m ^2) [see Clinical Studies (14.1)]. These patients had less overall glycemic efficacy, and patients treated with 300 mg per day had increases in serum potassium, which were transient and similar by the end of the trial. Patients with renal impairment using INVOKANA for glycemic control may also be more likely to experience hypotension and may be at higher risk for acute kidney injury [see Warnings and Precautions (5.3)].

Efficacy and safety trials with INVOKANA did not enroll adult patients with ESKD on dialysis or patients with an eGFR less than 30 mL/min/1.73 m ^2 [see Clinical Pharmacology (12.3)].

8.7 Hepatic Impairment

No dosage adjustment is necessary in patients with mild or moderate hepatic impairment. The use of INVOKANA has not been studied in patients with severe hepatic impairment and is therefore not recommended [see Clinical Pharmacology (12.3)].

10 OVERDOSAGE

In the event of an overdose, contact the Poison Help line (1-800-222-1222) or a medical toxicologist for additional overdosage management recommendations. It is also reasonable to employ the usual supportive measures, e.g., remove unabsorbed material from the gastrointestinal tract, employ clinical monitoring, and institute supportive treatment as dictated by the patient's clinical status. Canagliflozin was negligibly removed during a 4-hour hemodialysis session. Canagliflozin is not expected to be dialyzable by peritoneal dialysis.

11 DESCRIPTION

INVOKANA ®(canagliflozin) contains canagliflozin, an inhibitor of SGLT2, the transporter responsible for reabsorbing the majority of glucose filtered by the kidney. Canagliflozin, the active ingredient of INVOKANA, is chemically known as (1 S)-1,5-anhydro-1-[3-[[5-(4-fluorophenyl)-2-thienyl]methyl]-4-methylphenyl]-D-glucitol hemihydrate and its molecular formula and weight are C 24H 25FO 5S∙1/2 H 2O and 453.53, respectively. The structural formula for canagliflozin is:

Canagliflozin is practically insoluble in aqueous media from pH 1.1 to 12.9.

INVOKANA is supplied as film-coated tablets for oral administration, containing 102 and 306 mg of canagliflozin in each tablet strength, corresponding to 100 mg and 300 mg of canagliflozin (anhydrous), respectively.

Inactive ingredients of the core tablet are croscarmellose sodium (E468), hydroxypropyl cellulose (E463), lactose anhydrous, magnesium stearate (E572), and microcrystalline cellulose (E460[i]). The magnesium stearate is vegetable-sourced. The tablets are finished with a commercially available film-coating consisting of the following excipients: iron oxide yellow (E172) (100 mg tablet only), macrogol/PEG3350 (E1521), polyvinyl alcohol (E1203) (partially hydrolyzed), talc (E553b), and titanium dioxide (E171).

12 CLINICAL PHARMACOLOGY

12.1 Mechanism of Action

SGLT2, expressed in the proximal renal tubules, is responsible for the majority of the reabsorption of filtered glucose from the tubular lumen. Canagliflozin is an inhibitor of SGLT2. By inhibiting SGLT2, canagliflozin reduces reabsorption of filtered glucose and lowers the renal threshold for glucose (RT G), and thereby increases urinary glucose excretion (UGE).

Canagliflozin increases the delivery of sodium to the distal tubule by blocking SGLT2-dependent glucose and sodium reabsorption. This is believed to increase tubuloglomerular feedback and reduce intraglomerular pressure.

12.2 Pharmacodynamics

Following single and multiple oral doses of canagliflozin in adult patients with type 2 diabetes, dose-dependent decreases in RT G and increases in urinary glucose excretion were observed. From a starting RT G value of approximately 240 mg/dL, canagliflozin at 100 mg and 300 mg once daily suppressed RT G throughout the 24-hour period. Data from single oral doses of canagliflozin in healthy volunteers indicate that, on average, the elevation in urinary glucose excretion approaches baseline by about 3 days for doses up to 300 mg once daily. Maximal suppression of mean RT G over the 24-hour period was seen with the 300 mg daily dose to approximately 70 to 90 mg/dL in patients with type 2 diabetes in Phase 1 trials. The reductions in RT G led to increases in mean UGE of approximately 100 g/day in patients with type 2 diabetes treated with either 100 mg or 300 mg of canagliflozin. In patients with type 2 diabetes given 100 to 300 mg once daily over a 16-day dosing period, reductions in RT G and increases in urinary glucose excretion were observed over the dosing period. In this trial, plasma glucose declined in a dose-dependent fashion within the first day of dosing. In single-dose trials in healthy and type 2 diabetic patients, treatment with canagliflozin 300 mg before a mixed-meal delayed intestinal glucose absorption and reduced postprandial glucose.

Cardiac Electrophysiology

In a randomized, double-blind, placebo-controlled, active-comparator, 4-way crossover trial, 60 healthy adult subjects were administered a single oral dose of canagliflozin 300 mg, canagliflozin 1,200 mg (4 times the maximum recommended dose), moxifloxacin, and placebo. No meaningful changes in QTc interval were observed with either the recommended dose of 300 mg or the 1,200 mg dose.

12.3 Pharmacokinetics

The pharmacokinetics of canagliflozin is similar in healthy subjects and patients with type 2 diabetes. Following single-dose oral administration of 100 mg and 300 mg of INVOKANA, peak plasma concentrations (median T max) of canagliflozin occurs within 1 to 2 hours post-dose. Plasma C max and AUC of canagliflozin increased in a dose-proportional manner from 50 mg to 300 mg. The apparent terminal half-life (t 1/2) was 10.6 hours and 13.1 hours for the 100 mg and 300 mg doses, respectively. Steady-state was reached after 4 to 5 days of once-daily dosing with canagliflozin 100 mg to 300 mg. Canagliflozin does not exhibit time-dependent pharmacokinetics and accumulated in plasma up to 36% following multiple doses of 100 mg and 300 mg.

Absorption

The mean absolute oral bioavailability of canagliflozin is approximately 65%. Co-administration of a high-fat meal with canagliflozin had no effect on the pharmacokinetics of canagliflozin; therefore, INVOKANA may be taken with or without food. However, based on the potential to reduce postprandial plasma glucose excursions due to delayed intestinal glucose absorption, it is recommended that INVOKANA be taken before the first meal of the day [see Dosage and Administration (2.2)].

Distribution

The mean steady-state volume of distribution of canagliflozin following a single intravenous infusion in healthy subjects was 83.5 L, suggesting extensive tissue distribution. Canagliflozin is extensively bound to proteins in plasma (99%), mainly to albumin. Protein binding is independent of canagliflozin plasma concentrations. Plasma protein binding is not meaningfully altered in patients with renal or hepatic impairment.

Metabolism

O-glucuronidation is the major metabolic elimination pathway for canagliflozin, which is mainly glucuronidated by UGT1A9 and UGT2B4 to two inactive O-glucuronide metabolites.

CYP3A4-mediated (oxidative) metabolism of canagliflozin is minimal (approximately 7%) in humans.

Excretion

Following administration of a single oral [^14C] canagliflozin dose to healthy subjects, 41.5%, 7.0%, and 3.2% of the administered radioactive dose was recovered in feces as canagliflozin, a hydroxylated metabolite, and an O-glucuronide metabolite, respectively. Enterohepatic circulation of canagliflozin was negligible.

Approximately 33% of the administered radioactive dose was excreted in urine, mainly as O-glucuronide metabolites (30.5%). Less than 1% of the dose was excreted as unchanged canagliflozin in urine. Renal clearance of canagliflozin 100 mg and 300 mg doses ranged from 1.30 to 1.55 mL/min.

Mean systemic clearance of canagliflozin was approximately 192 mL/min in healthy subjects following intravenous administration.

Specific Populations

Pediatric Patients

The pharmacokinetics and pharmacodynamics of canagliflozin were investigated in pediatric patients aged 10 years and older with type 2 diabetes mellitus. Oral administration of canagliflozin at 100 mg and 300 mg resulted in exposures and responses consistent with those found in adult patients.

Patients with Renal Impairment

A single-dose, open-label trial evaluated the pharmacokinetics of canagliflozin 200 mg in adult subjects with varying degrees of renal impairment (classified using the MDRD-eGFR formula) compared to healthy subjects.

Renal impairment did not affect the C max of canagliflozin. Compared to healthy adult subjects (N=3; eGFR greater than or equal to 90 mL/min/1.73 m ^2), plasma AUC of canagliflozin was increased by approximately 15%, 29%, and 53% in subjects with mild (N=10), moderate (N=9), and severe (N=10) renal impairment, respectively, (eGFR 60 to less than 90, 30 to less than 60, and 15 to less than 30 mL/min/1.73 m ^2, respectively), but was similar for ESKD (N=8) subjects and healthy subjects.

Increases in canagliflozin AUC of this magnitude are not considered clinically relevant. The glucose lowering pharmacodynamic response to canagliflozin declines with increasing severity of renal impairment [see Contraindications (4)and Warnings and Precautions (5.3)].

Canagliflozin was negligibly removed by hemodialysis.

Patients with Hepatic Impairment

Relative to adult subjects with normal hepatic function, the geometric mean ratios for C max and AUC ∞ of canagliflozin were 107% and 110%, respectively, in subjects with Child-Pugh class A (mild hepatic impairment) and 96% and 111%, respectively, in subjects with Child-Pugh class B (moderate hepatic impairment) following administration of a single 300 mg dose of canagliflozin.

These differences are not considered to be clinically meaningful. There is no clinical experience in adult patients with Child-Pugh class C (severe) hepatic impairment [see Use in Specific Populations (8.7)].

Pharmacokinetic Effects of Age, Body Mass Index (BMI)/Weight, Gender and Race

Based on the population PK analysis with data collected from 1,526 adult subjects, age, body mass index (BMI)/weight, gender, and race do not have a clinically meaningful effect on the pharmacokinetics of canagliflozin [see Use in Specific Populations (8.5)].

Drug Interaction Studies

In Vitro Assessment of Drug Interactions

Canagliflozin did not induce CYP450 enzyme expression (3A4, 2C9, 2C19, 2B6, and 1A2) in cultured human hepatocytes. Canagliflozin did not inhibit the CYP450 isoenzymes (1A2, 2A6, 2C19, 2D6, or 2E1) and weakly inhibited CYP2B6, CYP2C8, CYP2C9, and CYP3A4 based on in vitro studies with human hepatic microsomes. Canagliflozin is a weak inhibitor of P-gp.

Canagliflozin is also a substrate of drug transporters P-glycoprotein (P-gp) and MRP2.

In Vivo Assessment of Drug Interactions

Table 8: Effect of Co–Administered Drugs on Systemic Exposures of Canagliflozin
Co-Administered Drug | Dose of Co-Administered Drug [Single dose unless otherwise noted] | Dose of Canagliflozin | Geometric Mean Ratio (Ratio With/Without Co-Administered Drug) No Effect = 1.0
Co-Administered Drug | Dose of Co-Administered Drug [Single dose unless otherwise noted] | Dose of Canagliflozin | AUC [AUC inf for drugs given as a single dose and AUC 24h for drugs given as multiple doses] (90% CI) | C max (90% CI)
See Drug Interactions (7)for the clinical relevance of the following:
Rifampin | 600 mg QD for 8 days | 300 mg | 0.49 (0.44; 0.54) | 0.72 (0.61; 0.84)
No dose adjustments of INVOKANA required for the following:
Cyclosporine | 400 mg | 300 mg QD for 8 days | 1.23 (1.19; 1.27) | 1.01 (0.91; 1.11)
Ethinyl estradiol and levonorgestrel | 0.03 mg ethinyl estradiol and 0.15 mg levonorgestrel | 200 mg QD for 6 days | 0.91 (0.88; 0.94) | 0.92 (0.84; 0.99)
Hydrochlorothiazide | 25 mg QD for 35 days | 300 mg QD for 7 days | 1.12 (1.08; 1.17) | 1.15 (1.06; 1.25)
Metformin HCl | 2,000 mg | 300 mg QD for 8 days | 1.10 (1.05; 1.15) | 1.05 (0.96; 1.16)
Probenecid | 500 mg BID for 3 days | 300 mg QD for 17 days | 1.21 (1.16; 1.25) | 1.13 (1.00; 1.28)
QD = once daily; BID = twice daily

Table 9: Effect of Canagliflozin on Systemic Exposure of Co-Administered Drugs
Co-Administered Drug | Dose of Co-Administered Drug [Single dose unless otherwise noted] | Dose of Canagliflozin | Geometric Mean Ratio (Ratio With/Without Co-Administered Drug) No Effect = 1.0
Co-Administered Drug | Dose of Co-Administered Drug [Single dose unless otherwise noted] | Dose of Canagliflozin |  | AUC [AUC inf for drugs given as a single dose and AUC 24h for drugs given as multiple doses] (90% CI) | C max (90% CI)
See Drug Interactions (7)for the clinical relevance of the following:
Digoxin | 0.5 mg QD first day followed by 0.25 mg QD for 6 days | 300 mg QD for 7 days | Digoxin | 1.20 (1.12; 1.28) | 1.36 (1.21; 1.53)
No dose adjustments of co-administered drug required for the following:
Acetaminophen | 1,000 mg | 300 mg BID for 25 days | Acetaminophen | 1.06 [AUC 0–12h] (0.98; 1.14) | 1.00 (0.92; 1.09)
Ethinyl estradiol and levonorgestrel | 0.03 mg ethinyl estradiol and 0.15 mg levonorgestrel | 200 mg QD for 6 days | ethinyl estradiol | 1.07 (0.99; 1.15) | 1.22 (1.10; 1.35)
Ethinyl estradiol and levonorgestrel | 0.03 mg ethinyl estradiol and 0.15 mg levonorgestrel | 200 mg QD for 6 days | Levonorgestrel | 1.06 (1.00; 1.13) | 1.22 (1.11; 1.35)
Glyburide | 1.25 mg | 200 mg QD for 6 days | Glyburide | 1.02 (0.98; 1.07) | 0.93 (0.85; 1.01)
Glyburide | 1.25 mg | 200 mg QD for 6 days | 3-cis-hydroxy-glyburide | 1.01 (0.96; 1.07) | 0.99 (0.91; 1.08)
Glyburide | 1.25 mg | 200 mg QD for 6 days | 4-trans-hydroxy-glyburide | 1.03 (0.97; 1.09) | 0.96 (0.88; 1.04)
Hydrochlorothiazide | 25 mg QD for 35 days | 300 mg QD for 7 days | Hydrochlorothiazide | 0.99 (0.95; 1.04) | 0.94 (0.87; 1.01)
Metformin HCl | 2,000 mg | 300 mg QD for 8 days | Metformin HCl | 1.20 (1.08; 1.34) | 1.06 (0.93; 1.20)
Simvastatin | 40 mg | 300 mg QD for 7 days | Simvastatin | 1.12 (0.94; 1.33) | 1.09 (0.91; 1.31)
Simvastatin | 40 mg | 300 mg QD for 7 days | simvastatin acid | 1.18 (1.03; 1.35) | 1.26 (1.10; 1.45)
Warfarin | 30 mg | 300 mg QD for 12 days | (R)-warfarin | 1.01 (0.96; 1.06) | 1.03 (0.94; 1.13)
Warfarin | 30 mg | 300 mg QD for 12 days | (S)-warfarin | 1.06 (1.00; 1.12) | 1.01 (0.90; 1.13)
Warfarin | 30 mg | 300 mg QD for 12 days | INR | 1.00 (0.98; 1.03) | 1.05 (0.99; 1.12)
QD = once daily; BID = twice daily; INR = International Normalized Ratio

13 NONCLINICAL TOXICOLOGY

13.1 Carcinogenesis, Mutagenesis, Impairment of Fertility

Carcinogenesis

Carcinogenicity was evaluated in 2-year studies conducted in CD1 mice and Sprague-Dawley rats. Canagliflozin did not increase the incidence of tumors in mice dosed at 10, 30, or 100 mg/kg (less than or equal to 14 times exposure from a 300 mg clinical dose).

Testicular Leydig cell tumors, considered secondary to increased luteinizing hormone (LH), increased significantly in male rats at all doses tested (10, 30, and 100 mg/kg). In a 12-week clinical trial, LH did not increase in males treated with canagliflozin.

Renal tubular adenoma and carcinoma increased significantly in male and female rats dosed at 100 mg/kg, or approximately 12-times exposure from a 300 mg clinical dose. Also, adrenal pheochromocytoma increased significantly in males and numerically in females dosed at 100 mg/kg. Carbohydrate malabsorption associated with high doses of canagliflozin was considered a necessary proximal event in the emergence of renal and adrenal tumors in rats. Clinical trials have not demonstrated carbohydrate malabsorption in humans at canagliflozin doses of up to 2-times the recommended clinical dose of 300 mg.

Mutagenesis

Canagliflozin was not mutagenic with or without metabolic activation in the Ames assay. Canagliflozin was mutagenic in the in vitro mouse lymphoma assay with but not without metabolic activation. Canagliflozin was not mutagenic or clastogenic in an in vivo oral micronucleus assay in rats and an in vivo oral Comet assay in rats.

Impairment of Fertility

Canagliflozin had no effects on the ability of rats to mate and sire or maintain a litter up to the high dose of 100 mg/kg (approximately 14 times and 18 times the 300 mg clinical dose in males and females, respectively), although there were minor alterations in a number of reproductive parameters (decreased sperm velocity, increased number of abnormal sperm, slightly fewer corpora lutea, fewer implantation sites, and smaller litter sizes) at the highest dosage administered.

14 CLINICAL STUDIES

14.1 Glycemic Control Trials in Adults with Type 2 Diabetes Mellitus

INVOKANA (canagliflozin) has been studied as monotherapy, in combination with metformin HCl, sulfonylurea, metformin HCl and sulfonylurea, metformin HCl and sitagliptin, metformin HCl and a thiazolidinedione (i.e., pioglitazone), and in combination with insulin (with or without other anti-hyperglycemic agents). The efficacy of INVOKANA was compared to a dipeptidyl peptidase-4 (DPP-4) inhibitor (sitagliptin), both as add-on combination therapy with metformin HCl and sulfonylurea, and a sulfonylurea (glimepiride), both as add-on combination therapy with metformin HCl. INVOKANA was also evaluated in adults 55 to 80 years of age and patients with moderate renal impairment.

Monotherapy

A total of 584 adult patients with type 2 diabetes inadequately controlled on diet and exercise participated in a 26-week double-blind, placebo-controlled trial to evaluate the efficacy and safety of INVOKANA. The mean age was 55 years, 44% of patients were male, and the mean baseline eGFR was 87 mL/min/1.73 m ^2. Patients taking other antihyperglycemic agents (N=281) discontinued the agent and underwent an 8-week washout followed by a 2-week, single-blind, placebo run-in period. Patients not taking oral antihyperglycemic agents (N=303) entered the 2-week, single-blind, placebo run-in period directly. After the placebo run-in period, patients were randomized to INVOKANA 100 mg, INVOKANA 300 mg, or placebo, administered once daily for 26 weeks.

At the end of treatment, INVOKANA 100 mg and 300 mg once daily resulted in a statistically significant improvement in HbA 1C(p<0.001 for both doses) compared to placebo. INVOKANA 100 mg and 300 mg once daily also resulted in a greater proportion of patients achieving an HbA 1Cless than 7%, in significant reduction in fasting plasma glucose (FPG), in improved postprandial glucose (PPG), and in percent body weight reduction compared to placebo (see Table 10). Statistically significant (p<0.001 for both doses) mean changes from baseline in systolic blood pressure relative to placebo were -3.7 mmHg and -5.4 mmHg with INVOKANA 100 mg and 300 mg, respectively.

Table 10: Results from 26-Week Placebo-Controlled Clinical Trial with INVOKANA as Monotherapy in Adults with Type 2 Diabetes Mellitus [Intent-to-treat population using last observation in the trial prior to glycemic rescue therapy]
Efficacy Parameter | Placebo (N=192) | INVOKANA 100 mg (N=195) | INVOKANA 300 mg (N=197)
HbA 1C(%)
Baseline (mean) | 7.97 | 8.06 | 8.01
Change from baseline (adjusted mean) | 0.14 | -0.77 | -1.03
Difference from placebo (adjusted mean) (95% CI) [Least squares mean adjusted for baseline value and stratification factors] |  | -0.91 [p<0.001] (-1.09; -0.73) | -1.16 (-1.34; -0.99)
Percent of Patients Achieving HbA 1C< 7% | 21 | 45 | 62
Fasting Plasma Glucose (mg/dL)
Baseline (mean) | 166 | 172 | 173
Change from baseline (adjusted mean) | 8 | -27 | -35
Difference from placebo (adjusted mean) (95% CI) |  | -36 (-42; -29) | -43 (-50; -37)
2-hour Postprandial Glucose (mg/dL)
Baseline (mean) | 229 | 250 | 254
Change from baseline (adjusted mean) | 5 | -43 | -59
Difference from placebo (adjusted mean) (95% CI) |  | -48 (-59.1; -37.0) | -64 (-75.0; -52.9)
Body Weight
Baseline (mean) in kg | 87.5 | 85.9 | 86.9
% change from baseline (adjusted mean) | -0.6 | -2.8 | -3.9
Difference from placebo (adjusted mean) (95% CI) |  | -2.2 (-2.9; -1.6) | -3.3 (-4.0; -2.6)

Add-on Combination Therapy with Metformin HCl

A total of 1,284 adult patients with type 2 diabetes inadequately controlled on metformin HCl monotherapy (greater than or equal to 2,000 mg/day, or at least 1,500 mg/day if higher dose not tolerated) participated in a 26-week, double-blind, placebo- and active-controlled trial to evaluate the efficacy and safety of INVOKANA in combination with metformin HCl. The mean age was 55 years, 47% of patients were male, and the mean baseline eGFR was 89 mL/min/1.73 m ^2. Patients already on the required metformin HCl dose (N=1,009) were randomized after completing a 2-week, single-blind, placebo run-in period. Patients taking less than the required metformin HCl dose or patients on metformin HCl in combination with another antihyperglycemic agent (N=275) were switched to metformin HCl monotherapy (at doses described above) for at least 8 weeks before entering the 2-week, single-blind, placebo run-in. After the placebo run-in period, patients were randomized to INVOKANA 100 mg, INVOKANA 300 mg, sitagliptin 100 mg, or placebo, administered once daily as add-on therapy to metformin HCl.

At the end of treatment, INVOKANA 100 mg and 300 mg once daily resulted in a statistically significant improvement in HbA 1C(p<0.001 for both doses) compared to placebo when added to metformin HCl. INVOKANA 100 mg and 300 mg once daily also resulted in a greater proportion of patients achieving an HbA 1Cless than 7%, in significant reduction in fasting plasma glucose (FPG), in improved postprandial glucose (PPG), and in percent body weight reduction compared to placebo when added to metformin HCl (see Table 11). Statistically significant (p<0.001 for both doses) mean changes from baseline in systolic blood pressure relative to placebo were -5.4 mmHg and -6.6 mmHg with INVOKANA 100 mg and 300 mg, respectively.

Table 11: Results from 26-Week Placebo-Controlled Clinical Trial of INVOKANA in Combination with Metformin HCl in Adults with Type 2 Diabetes Mellitus [Intent-to-treat population using last observation in the trial prior to glycemic rescue therapy]
Efficacy Parameter | Placebo + Metformin HCl (N=183) | INVOKANA 100 mg + Metformin HCl (N=368) | INVOKANA 300 mg + Metformin HCl (N=367)
HbA 1C(%)
Baseline (mean) | 7.96 | 7.94 | 7.95
Change from baseline (adjusted mean) | -0.17 | -0.79 | -0.94
Difference from placebo (adjusted mean) (95% CI) [Least squares mean adjusted for baseline value and stratification factors] |  | -0.62 [p<0.001] (-0.76; -0.48) | -0.77 (-0.91; -0.64)
Percent of patients achieving HbA 1C< 7% | 30 | 46 | 58
Fasting Plasma Glucose (mg/dL)
Baseline (mean) | 164 | 169 | 173
Change from baseline (adjusted mean) | 2 | -27 | -38
Difference from placebo (adjusted mean) (95% CI) |  | -30 (-36; -24) | -40 (-46; -34)
2-hour Postprandial Glucose (mg/dL)
Baseline (mean) | 249 | 258 | 262
Change from baseline (adjusted mean) | -10 | -48 | -57
Difference from placebo (adjusted mean) (95% CI) |  | -38 (-49; -27) | -47 (-58; -36)
Body Weight
Baseline (mean) in kg | 86.7 | 88.7 | 85.4
% change from baseline (adjusted mean) | -1.2 | -3.7 | -4.2
Difference from placebo (adjusted mean) (95% CI) |  | -2.5 (-3.1; -1.9) | -2.9 (-3.5; -2.3)

Initial Combination Therapy with Metformin HCl Extended-Release

A total of 1,186 adult patients with type 2 diabetes inadequately controlled with diet and exercise participated in a 26-week double-blind, active-controlled, parallel-group, 5-arm, multicenter trial to evaluate the efficacy and safety of initial therapy with INVOKANA in combination with metformin HCl extended-release. The median age was 56 years, 48% of patients were male, and the mean baseline eGFR was 87.6 mL/min/1.73 m ^2. The median duration of diabetes was 1.6 years, and 72% of patients were treatment naïve. After completing a 2-week single-blind placebo run-in period, patients were randomly assigned for a double-blind treatment period of 26 weeks to 1 of 5 treatment groups (Table 12). The metformin HCl extended-release dose was initiated at 500 mg/day for the first week of treatment and then increased to 1,000 mg/day. Metformin HCl extended-release or matching placebo was up-titrated every 2–3 weeks during the next 8 weeks of treatment to a maximum daily dose of 1,500 to 2,000 mg/day, as tolerated; about 90% of patients reached 2,000 mg/day.

At the end of treatment, INVOKANA 100 mg and INVOKANA 300 mg in combination with metformin HCl extended-release resulted in a statistically significant greater improvement in HbA 1Ccompared to their respective INVOKANA doses (100 mg and 300 mg) alone or metformin HCl extended-release alone.

Table 12: Results from 26-Week Active-Controlled Clinical Trial of INVOKANA Alone or INVOKANA as Initial Combination Therapy with Metformin HCl Extended-Release in Adults with Type 2 Diabetes Mellitus [Intent-to-treat population]
Efficacy Parameter | Metformin HCl extended-release (N=237) | INVOKANA 100 mg (N=237) | INVOKANA 300 mg (N=238) | INVOKANA 100 mg + Metformin HCl extended-release (N=237) | INVOKANA 300 mg + Metformin HCl extended-release (N=237)
HbA 1C(%)
Baseline (mean) | 8.81 | 8.78 | 8.77 | 8.83 | 8.90
Change from baseline (adjusted mean) [There were 121 patients without week 26 efficacy data. Analyses addressing missing data gave consistent results with the results provided in this table.] | -1.30 | -1.37 | -1.42 | -1.77 | -1.78
Difference from canagliflozin 100 mg (adjusted mean) (95% CI) [Least squares mean adjusted for covariates including baseline value and stratification factor] |  |  |  | -0.40 [Adjusted p=0.001 for superiority] (-0.59, -0.21)
Difference from canagliflozin 300 mg (adjusted mean) (95% CI) |  |  |  |  | -0.36 (-0.56, -0.17)
Difference from metformin HCl extended-release (adjusted mean) (95% CI) |  | -0.06 [Adjusted p=0.001 for non-inferiority] (-0.26, 0.13) | -0.11 (-0.31, 0.08) | -0.46 (-0.66, -0.27) | -0.48 (-0.67, -0.28)
Percent of patients achieving HbA 1C< 7% | 38 | 34 | 39 | 47 [Adjusted p<0.05] | 51

INVOKANA Compared to Glimepiride, Both as Add-on Combination With Metformin HCl

A total of 1,450 adult patients with type 2 diabetes inadequately controlled on metformin HCl monotherapy (greater than or equal to 2,000 mg/day, or at least 1,500 mg/day if higher dose not tolerated) participated in a 52-week, double-blind, active-controlled trial to evaluate the efficacy and safety of INVOKANA in combination with metformin HCl.

The mean age was 56 years, 52% of patients were male, and the mean baseline eGFR was 90 mL/min/1.73 m ^2. Patients tolerating maximally required metformin HCl dose (N=928) were randomized after completing a 2-week, single-blind, placebo run-in period. Other patients (N=522) were switched to metformin HCl monotherapy (at doses described above) for at least 10 weeks, then completed a 2-week single-blind run-in period. After the 2-week run-in period, patients were randomized to INVOKANA 100 mg, INVOKANA 300 mg, or glimepiride (titration allowed throughout the 52-week trial to 6 or 8 mg), administered once daily as add-on therapy to metformin HCl.

As shown in Table 13 and Figure 1, at the end of treatment, INVOKANA 100 mg provided similar reductions in HbA 1Cfrom baseline compared to glimepiride when added to metformin HCl therapy. INVOKANA 300 mg provided a greater reduction from baseline in HbA 1C compared to glimepiride, and the relative treatment difference was -0.12% (95% CI: –0.22; –0.02). As shown in Table 13, treatment with INVOKANA 100 mg and 300 mg daily provided greater improvements in percent body weight change, relative to glimepiride.

Table 13: Results from 52–Week Clinical Trial Comparing INVOKANA to Glimepiride in Combination with Metformin HCl in Adults with Type 2 Diabetes Mellitus [Intent-to-treat population using last observation in the trial prior to glycemic rescue therapy]
Efficacy Parameter | INVOKANA 100 mg + Metformin HCl (N=483) | INVOKANA 300 mg + Metformin HCl (N=485) | Glimepiride (titrated) + Metformin HCl (N=482)
HbA 1C(%)
Baseline (mean) | 7.78 | 7.79 | 7.83
Change from baseline (adjusted mean) | -0.82 | -0.93 | -0.81
Difference from glimepiride (adjusted mean) (95% CI) [Least squares mean adjusted for baseline value and stratification factors] | -0.01 [INVOKANA + metformin HCl is considered non-inferior to glimepiride + metformin HCl because the upper limit of this confidence interval is less than the pre-specified non-inferiority margin of < 0.3%.] (-0.11; 0.09) | -0.12 (-0.22; -0.02)
Percent of patients achieving HbA 1C< 7% | 54 | 60 | 56
Fasting Plasma Glucose (mg/dL)
Baseline (mean) | 165 | 164 | 166
Change from baseline (adjusted mean) | -24 | -28 | -18
Difference from glimepiride (adjusted mean) (95% CI) | -6 (-10; -2) | -9 (-13; -5)
Body Weight
Baseline (mean) in kg | 86.8 | 86.6 | 86.6
% change from baseline (adjusted mean) | -4.2 | -4.7 | 1.0
Difference from glimepiride (adjusted mean) (95% CI) | -5.2 [p<0.001] (-5.7; -4.7) | -5.7 (-6.2; -5.1)

Figure 1: Mean HbA 1C Change in Adults with Type 2 Diabetes Mellitus Treated with INVOKANA or Glimepiride in Combination with Metformin HCl at Each Time Point (Completers) and at Week 52 Using Last Observation Carried Forward (mITT Population)

Add-on Combination Therapy with Sulfonylurea

A total of 127 adult patients with type 2 diabetes inadequately controlled on sulfonylurea monotherapy participated in an 18-week, double-blind, placebo-controlled sub-trial to evaluate the efficacy and safety of INVOKANA in combination with sulfonylurea. The mean age was 65 years, 57% of patients were male, and the mean baseline eGFR was 69 mL/min/1.73 m ^2. Patients treated with sulfonylurea monotherapy on a stable protocol-specified dose (greater than or equal to 50% maximal dose) for at least 10 weeks completed a 2-week, single-blind, placebo run-in period. After the run-in period, patients with inadequate glycemic control were randomized to INVOKANA 100 mg, INVOKANA 300 mg, or placebo, administered once daily as add-on to sulfonylurea.

As shown in Table 14, at the end of treatment, INVOKANA 100 mg and 300 mg daily provided statistically significant (p<0.001 for both doses) improvements in HbA 1C relative to placebo when added to sulfonylurea. INVOKANA 300 mg once daily compared to placebo resulted in a greater proportion of patients achieving an HbA 1C less than 7%, (33% vs 5%), greater reductions in fasting plasma glucose (-36 mg/dL vs +12 mg/dL), and greater percent body weight reduction (-2.0% vs -0.2%).

Table 14: Results from 18-Week Placebo–Controlled Clinical Trial of INVOKANA in Combination with Sulfonylurea in Adults with Type 2 Diabetes Mellitus [Intent-to-treat population using last observation in the trial prior to glycemic rescue therapy]
Efficacy Parameter | Placebo + Sulfonylurea (N=45) | INVOKANA 100 mg + Sulfonylurea (N=42) | INVOKANA 300 mg + Sulfonylurea (N=40)
HbA 1C(%)
Baseline (mean) | 8.49 | 8.29 | 8.28
Change from baseline (adjusted mean) | 0.04 | -0.70 | -0.79
Difference from placebo (adjusted mean) (95% CI) [Least squares mean adjusted for baseline value] |  | -0.74 [p<0.001] (-1.15; -0.33) | -0.83 (-1.24; -0.41)

Add-on Combination Therapy with Metformin HCl and Sulfonylurea

A total of 469 adult patients with type 2 diabetes inadequately controlled on the combination of metformin HCl (greater than or equal to 2,000 mg/day or at least 1,500 mg/day if higher dose not tolerated) and sulfonylurea (maximal or near-maximal effective dose) participated in a 26-week, double-blind, placebo-controlled trial to evaluate the efficacy and safety of INVOKANA in combination with metformin HCl and sulfonylurea. The mean age was 57 years, 51% of patients were male, and the mean baseline eGFR was 89 mL/min/1.73 m ^2. Patients already on the protocol-specified doses of metformin HCl and sulfonylurea (N=372) entered a 2-week, single-blind, placebo run-in period. Other patients (N=97) were required to be on a stable protocol-specified dose of metformin HCl and sulfonylurea for at least 8 weeks before entering the 2-week run-in period. Following the run-in period, patients were randomized to INVOKANA 100 mg, INVOKANA 300 mg, or placebo, administered once daily as add-on to metformin HCl and sulfonylurea.

At the end of treatment, INVOKANA 100 mg and 300 mg once daily resulted in a statistically significant improvement in HbA 1C (p<0.001 for both doses) compared to placebo when added to metformin HCl and sulfonylurea. INVOKANA 100 mg and 300 mg once daily also resulted in a greater proportion of patients achieving an HbA 1C less than 7%, in a significant reduction in fasting plasma glucose (FPG), and in percent body weight reduction compared to placebo when added to metformin HCl and sulfonylurea (see Table 15).

Table 15: Results from 26-Week Placebo-Controlled Clinical Trial of INVOKANA in Combination with Metformin HCl and Sulfonylurea in Adults with Type 2 Diabetes Mellitus [Intent-to-treat population using last observation in the trial prior to glycemic rescue therapy]
Efficacy Parameter | Placebo + Metformin HCl and Sulfonylurea (N=156) | INVOKANA 100 mg + Metformin HCl and Sulfonylurea (N=157) | INVOKANA 300 mg + Metformin HCl and Sulfonylurea (N=156)
HbA 1C(%)
Baseline (mean) | 8.12 | 8.13 | 8.13
Change from baseline (adjusted mean) | -0.13 | -0.85 | -1.06
Difference from placebo (adjusted mean) (95% CI) [Least squares mean adjusted for baseline value and stratification factors] |  | -0.71 [p<0.001] (-0.90; -0.52) | -0.92 (-1.11; -0.73)
Percent of patients achieving A 1C< 7% | 18 | 43 | 57
Fasting Plasma Glucose (mg/dL)
Baseline (mean) | 170 | 173 | 168
Change from baseline (adjusted mean) | 4 | -18 | -31
Difference from placebo (adjusted mean) (95% CI) |  | -22 (-31; -13) | -35 (-44; -25)
Body Weight
Baseline (mean) in kg | 90.8 | 93.5 | 93.5
% change from baseline (adjusted mean) | -0.7 | -2.1 | -2.6
Difference from placebo (adjusted mean) (95% CI) |  | -1.4 (-2.1; -0.7) | -2.0 (-2.7; -1.3)

Add-on Combination Therapy with Metformin HCl and Sitagliptin

A total of 217 adult patients with type 2 diabetes inadequately controlled on the combination of metformin HCl (greater than or equal to 1,500 mg/day) and sitagliptin 100 mg/day (or equivalent fixed-dose combination) participated in a 26-week, double-blind, placebo-controlled trial to evaluate the efficacy and safety of INVOKANA in combination with metformin HCl and sitagliptin. The mean age was 57 years, 58% of patients were male, 73% of patients were White, 15% were Asian, and 12% were Black or African American. The mean baseline eGFR was 90 mL/min/1.73 m ^2 and the mean baseline BMI was 32 kg/m ^2. The mean duration of diabetes was 10 years. Eligible patients entered a 2-week, single-blind, placebo run-in period and were subsequently randomized to INVOKANA 100 mg or placebo, administered once daily as add-on to metformin HCl and sitagliptin. Patients with a baseline eGFR of 70 mL/min/1.73 m ^2 or greater who were tolerating INVOKANA 100 mg and who required additional glycemic control (fasting finger stick 100 mg/dL or greater at least twice within 2 weeks) were up-titrated to INVOKANA 300 mg. While up-titration occurred as early as Week 4, most (90%) patients randomized to INVOKANA were up-titrated to INVOKANA 300 mg by 6 to 8 weeks.

At the end of 26 weeks, INVOKANA resulted in a statistically significant improvement in HbA 1C (p<0.001) compared to placebo when added to metformin HCl and sitagliptin.

Table 16: Results from 26–Week Placebo-Controlled Clinical Trial of INVOKANA in Combination with Metformin HCl and Sitagliptin in Adults with Type 2 Diabetes Mellitus
Efficacy Parameter | Placebo + Metformin HCl and Sitagliptin (N=108 [To preserve the integrity of randomization, all randomized patients were included in the analysis. The patient who was randomized once to each arm was analyzed on INVOKANA.]) | INVOKANA + Metformin HCl and Sitagliptin (N=109)
HbA 1C(%)
Baseline (mean) | 8.40 | 8.50
Change from baseline (adjusted mean) | -0.03 | -0.83
Difference from placebo (adjusted mean) (95% CI) [Early treatment discontinuation before week 26, occurred in 11.0% and 24.1% of INVOKANA and placebo patients, respectively.] [Estimated using a multiple imputation method modeling a "wash-out" of the treatment effect for patients having missing data who discontinued treatment. Missing data was imputed only at week 26 and analyzed using ANCOVA.] |  | -0.81 [p<0.001] (-1.11; -0.51)
Percent of patients achieving HbA 1C< 7% [Patients without week 26 efficacy data were considered as non-responders when estimating the proportion achieving HbA 1C < 7%.] | 9 | 28
Fasting Plasma Glucose (mg/dL) [Estimated using a multiple imputation method modeling a "wash-out" of the treatment effect for patients having missing data who discontinued treatment. A mixed model for repeated measures was used to analyze the imputed data.]
Baseline (mean) | 180 | 185
Change from baseline (adjusted mean) | -3 | -28
Difference from placebo (adjusted mean) (95% CI) |  | -25 (-39; -11)

INVOKANA Compared to Sitagliptin, Both as Add-on Combination Therapy with Metformin HCl and Sulfonylurea

A total of 755 adult patients with type 2 diabetes inadequately controlled on the combination of metformin HCl (greater than or equal to 2,000 mg/day or at least 1,500 mg/day if higher dose not tolerated) and sulfonylurea (near-maximal or maximal effective dose) participated in a 52-week, double-blind, active-controlled trial to compare the efficacy and safety of INVOKANA 300 mg versus sitagliptin 100 mg in combination with metformin HCl and sulfonylurea. The mean age was 57 years, 56% of patients were male, and the mean baseline eGFR was 88 mL/min/1.73 m ^2. Patients already on protocol-specified doses of metformin HCl and sulfonylurea (N=716) entered a 2-week single-blind, placebo run-in period. Other patients (N=39) were required to be on a stable protocol-specified dose of metformin HCl and sulfonylurea for at least 8 weeks before entering the 2-week run-in period. Following the run-in period, patients were randomized to INVOKANA 300 mg or sitagliptin 100 mg as add-on to metformin HCl and sulfonylurea.

As shown in Table 17 and Figure 2, at the end of treatment, INVOKANA 300 mg provided greater HbA 1C reduction compared to sitagliptin 100 mg when added to metformin HCl and sulfonylurea (p<0.05). INVOKANA 300 mg resulted in a mean percent change in body weight from baseline of -2.5% compared to +0.3% with sitagliptin 100 mg. A mean change in systolic blood pressure from baseline of -5.06 mmHg was observed with INVOKANA 300 mg compared to +0.85 mmHg with sitagliptin 100 mg.

Table 17: Results from 52-Week Clinical Trial Comparing INVOKANA to Sitagliptin in Combination with Metformin HCl and Sulfonylurea in Adults with Type 2 Diabetes Mellitus [Intent-to-treat population using last observation in the trial prior to glycemic rescue therapy]
Efficacy Parameter | INVOKANA 300 mg + Metformin HCl and Sulfonylurea (N=377) | Sitagliptin 100 mg + Metformin HCl and Sulfonylurea (N=378)
HbA 1C(%)
Baseline (mean) | 8.12 | 8.13
Change from baseline (adjusted mean) | -1.03 | -0.66
Difference from sitagliptin (adjusted mean) (95% CI) [Least squares mean adjusted for baseline value and stratification factors] | -0.37 [INVOKANA + metformin HCl+ sulfonylurea is considered non-inferior to sitagliptin + metformin HCl + sulfonylurea because the upper limit of this confidence interval is less than the pre-specified non-inferiority margin of < 0.3%.] (-0.50; -0.25)
Percent of patients achieving HbA 1C< 7% | 48 | 35
Fasting Plasma Glucose (mg/dL)
Baseline (mean) | 170 | 164
Change from baseline (adjusted mean) | -30 | -6
Difference from sitagliptin (adjusted mean) (95% CI) | -24 (-30; -18)
Body Weight
Baseline (mean) in kg | 87.6 | 89.6
% change from baseline (adjusted mean) | -2.5 | 0.3
Difference from sitagliptin (adjusted mean) (95% CI) | -2.8 [p<0.001] (-3.3; -2.2)

Figure 2: Mean HbA 1CChange in Adults with Type 2 Diabetes Mellitus Treated with INVOKANA or Sitagliptin in Combination with Metformin HCl and Sulfonylurea at Each Time Point (Completers) and at Week 52 Using Last Observation Carried Forward (mITT Population)

Add-on Combination Therapy with Metformin HCl and Pioglitazone

A total of 342 adult patients with type 2 diabetes inadequately controlled on the combination of metformin HCl (greater than or equal to 2,000 mg/day or at least 1,500 mg/day if higher dose not tolerated) and pioglitazone (30 or 45 mg/day) participated in a 26-week, double-blind, placebo-controlled trial to evaluate the efficacy and safety of INVOKANA in combination with metformin HCl and pioglitazone. The mean age was 57 years, 63% of patients were male, and the mean baseline eGFR was 86 mL/min/1.73 m ^2. Patients already on protocol-specified doses of metformin HCl and pioglitazone (N=163) entered a 2-week, single-blind, placebo run-in period.

Other patients (N=181) were required to be on stable protocol-specified doses of metformin HCl and pioglitazone for at least 8 weeks before entering the 2-week run-in period. Following the run-in period, patients were randomized to INVOKANA 100 mg, INVOKANA 300 mg, or placebo, administered once daily as add-on to metformin HCl and pioglitazone.

At the end of treatment, INVOKANA 100 mg and 300 mg once daily resulted in a statistically significant improvement in HbA 1C(p<0.001 for both doses) compared to placebo when added to metformin HCl and pioglitazone. INVOKANA 100 mg and 300 mg once daily also resulted in a greater proportion of patients achieving an HbA 1Cless than 7%, in significant reduction in fasting plasma glucose (FPG) and in percent body weight reduction compared to placebo when added to metformin HCl and pioglitazone (see Table 18). Statistically significant (p<0.05 for both doses) mean changes from baseline in systolic blood pressure relative to placebo were -4.1 mmHg and -3.5 mmHg with INVOKANA 100 mg and 300 mg, respectively.

Table 18: Results from 26-Week Placebo-Controlled Clinical Trial of INVOKANA in Combination with Metformin HCl and Pioglitazone in Adults with Type 2 Diabetes Mellitus [Intent-to-treat population using last observation in the trial prior to glycemic rescue therapy]
Efficacy Parameter | Placebo + Metformin HCl and Pioglitazone (N=115) | INVOKANA 100 mg + Metformin HCl and Pioglitazone (N=113) | INVOKANA 300 mg + Metformin HCl and Pioglitazone (N=114)
HbA 1C(%)
Baseline (mean) | 8.00 | 7.99 | 7.84
Change from baseline (adjusted mean) | -0.26 | -0.89 | -1.03
Difference from placebo (adjusted mean) (95% CI) [Least squares mean adjusted for baseline value and stratification factors] |  | -0.62 [p<0.001] (-0.81; -0.44) | -0.76 (-0.95; -0.58)
Percent of patients achieving HbA 1C< 7% | 33 | 47 | 64
Fasting Plasma Glucose (mg/dL)
Baseline (mean) | 164 | 169 | 164
Change from baseline (adjusted mean) | 3 | -27 | -33
Difference from placebo (adjusted mean) (95% CI) |  | -29 (-37; -22) | -36 (-43; -28)
Body Weight
Baseline (mean) in kg | 94.0 | 94.2 | 94.4
% change from baseline (adjusted mean) | -0.1 | -2.8 | -3.8
Difference from placebo (adjusted mean) (95% CI) |  | -2.7 (-3.6; -1.8) | -3.7 (-4.6; -2.8)

Add-On Combination Therapy with Insulin (With or Without Other Antihyperglycemic Agents)

A total of 1,718 adult patients with type 2 diabetes inadequately controlled on insulin greater than or equal to 30 units/day or insulin in combination with other antihyperglycemic agents participated in an 18-week, double-blind, placebo-controlled subtrial of a cardiovascular trial to evaluate the efficacy and safety of INVOKANA in combination with insulin. The mean age was 63 years, 66% of patients were male, and the mean baseline eGFR was 75 mL/min/1.73 m^2. Patients on basal, bolus, or basal/bolus insulin for at least 10 weeks entered a 2-week, single-blind, placebo run-in period. Approximately 70% of patients were on a background basal/bolus insulin regimen. After the run-in period, patients were randomized to INVOKANA 100 mg, INVOKANA 300 mg, or placebo, administered once daily as add-on to insulin. The mean daily insulin dose at baseline was 83 units, which was similar across treatment groups.

At the end of treatment, INVOKANA 100 mg and 300 mg once daily resulted in a statistically significant improvement in HbA 1C(p<0.001 for both doses) compared to placebo when added to insulin. INVOKANA 100 mg and 300 mg once daily also resulted in a greater proportion of patients achieving an HbA 1Cless than 7%, in significant reductions in fasting plasma glucose (FPG), and in percent body weight reductions compared to placebo (see Table 19). Statistically significant (p<0.001 for both doses) mean changes from baseline in systolic blood pressure relative to placebo were -2.6 mmHg and -4.4 mmHg with INVOKANA 100 mg and 300 mg, respectively.

Table 19: Results from 18-Week Placebo-Controlled Clinical Trial of INVOKANA in Combination with Insulin ≥ 30 Units/Day (With or Without Other Oral Antihyperglycemic Agents) in Adults with Type 2 Diabetes Mellitus [Intent-to-treat population using last observation in the trial prior to glycemic rescue therapy]
Efficacy Parameter | Placebo + Insulin (N=565) | INVOKANA 100 mg + Insulin (N=566) | INVOKANA 300 mg + Insulin (N=587)
HbA 1C(%)
Baseline (mean) | 8.20 | 8.33 | 8.27
Change from baseline (adjusted mean) | 0.01 | -0.63 | -0.72
Difference from placebo (adjusted mean) (95% CI) [Least squares mean adjusted for baseline value and stratification factors] |  | -0.65 [p<0.001] (-0.73; -0.56) | -0.73 (-0.82; -0.65)
Percent of patients achieving HbA 1C< 7% | 8 | 20 | 25
Fasting Plasma Glucose (mg/dL)
Baseline | 169 | 170 | 168
Change from baseline (adjusted mean) | 4 | -19 | -25
Difference from placebo (adjusted mean) (97.5% CI) |  | -23 (-29; -16) | -29 (-35; -23)
Body Weight
Baseline (mean) in kg | 97.7 | 96.9 | 96.7
% change from baseline (adjusted mean) | 0.1 | -1.8 | -2.3
Difference from placebo (adjusted mean) (97.5% CI) |  | -1.9 (-2.2; -1.6) | -2.4 (-2.7; -2.1)

Trial in Patients Ages 55 to 80

A total of 714 type 2 diabetes patients ages 55 to 80 years and inadequately controlled on current diabetes therapy (either diet and exercise alone or in combination with oral or parenteral agents) participated in a 26-week, double-blind, placebo-controlled trial to evaluate the efficacy and safety of INVOKANA in combination with current diabetes treatment. The mean age was 64 years, 55% of patients were male, and the mean baseline eGFR was 77 mL/min/1.73 m ^2. Patients were randomized in a 1:1:1 ratio to the addition of INVOKANA 100 mg, INVOKANA 300 mg, or placebo, administered once daily. At the end of treatment, INVOKANA provided statistically significant improvements from baseline relative to placebo in HbA1C (p<0.001 for both doses) of -0.57% (95% CI: -0.71%; -0.44%) for INVOKANA 100 mg and -0.70% (95% CI: -0.84%; -0.57%) for INVOKANA 300 mg [see Use in Specific Populations (8.5)].

Glycemic Control in Patients with Moderate Renal Impairment

A total of 269 adult patients with type 2 diabetes and a baseline eGFR of 30 mL/min/1.73 m ^2 to less than 50 mL/min/1.73 m ^2 inadequately controlled on current diabetes therapy participated in a 26-week, double-blind, placebo-controlled clinical trial to evaluate the efficacy and safety of INVOKANA in combination with current diabetes treatment (diet or antihyperglycemic agent therapy, with 95% of patients on insulin and/or sulfonylurea). The mean age was 68 years, 61% of patients were male, and the mean baseline eGFR was 39 mL/min/1.73 m^2. Patients were randomized in a 1:1:1 ratio to the addition of INVOKANA 100 mg, INVOKANA 300 mg, or placebo, administered once daily.

At the end of treatment, INVOKANA 100 mg and INVOKANA 300 mg daily provided greater reductions in HbA 1Crelative to placebo (-0.30% [95% CI: -0.53%; -0.07%] and -0.40%, [95% CI: -0.64%; -0.17%], respectively) [see Warnings and Precautions (5.3), Adverse Reactions (6.1), Use in Specific Populations (8.6), and Clinical Studies (14.4)].

14.2 Glycemic Control Trial in Pediatric Patients Aged 10 Years and Older with Type 2 Diabetes Mellitus

In a double-blind, placebo-controlled, parallel-group pediatric trial (NCT03170518), 171 pediatric patients aged 10 to 17 years with inadequately controlled type 2 diabetes mellitus (HbA 1C≥6.5% and ≤11.0%) were randomized to INVOKANA (84 patients) or placebo (87 patients) as add-on to diet and exercise, metformin HCl (≥1,000 mg per day or maximally tolerated dosage), insulin, or a combination of metformin HCl and insulin, for a total of 52-weeks. At Week 13, patients in the INVOKANA arm whose HbA 1Cwas ≥7.0% and eGFR ≥60 mL/min/1.73 m ^2were re-randomized to either continue on INVOKANA 100 mg orally once daily (n=16) or to up-titrate to INVOKANA 300 mg orally once daily (n=17).

At baseline, background therapies included diet and exercise only (14%), insulin monotherapy (11%), metformin HCl and insulin (29%), and metformin HCl monotherapy (46%). The mean HbA 1Cat baseline was 8.0% and the mean duration of type 2 diabetes mellitus was 2 years. The mean eGFR at baseline was 157.3 mL/min/1.73 m ^2, and approximately 16% (24/151) of the trial population with measurements had microalbuminuria or macroalbuminuria. Patients with an eGFR less than 60 mL/min/1.73 m ^2were not enrolled in the trial; no patients in the trial reached an eGFR < 60 mL/min/1.73 m ^2. The mean age was 14.3 years, 47% were under 15 years of age, and 68% were female. Approximately 42% were Asian, 42% were White, 11% were Black or African American, 5% were American Indian/Alaska Native, and 36% were of Hispanic or Latino ethnicity. The mean BMI was 30.8 kg/m^2(range 18–57 kg/m ^2) and the mean BMI Z-score was 1.84.

At Week 26, treatment with canagliflozin provided statistically significant improvement in HbA 1Cfrom baseline, compared with placebo (see Table 20).

Table 20: Results at Week 26 in a Placebo-Controlled Trial of INVOKANA in Combination with Metformin HCl and/or Insulin or as Monotherapy in Pediatric Patients Aged 10 Years and Older with Type 2 Diabetes Mellitus [Modified intent-to-treat set (All randomized and treated patients with baseline HbA 1C measurement).]
Efficacy Parameter | Placebo (N=87) | INVOKANA (N=84)
HbA 1C(%)
Baseline (mean) | 8.3 | 7.8
Change from baseline [Multiple imputation using retrieved dropout approach with 1000 iterations for missing data (canagliflozin N=7 (8.3%), placebo N=7 (8.1%) for HbA 1C and canagliflozin N=9 (10.7%), placebo N=7 (8.1%) for FPG).] [Least-Square Mean from Analysis of Covariance (ANCOVA) adjusted for baseline value, baseline age stratum (< 15 years vs 15 to < 18 years) and baseline antihyperglycemic agent (AHA) background (i.e, diet and exercise only, metformin monotherapy, insulin monotherapy, or combination of insulin and metformin).] | 0.34 | -0.38
Difference from placebo 95% CI |  | -0.73 (-1.26, -0.19) [P-value=0.008 (two-sided)]
FPG (mg/dL)
Baseline (mean) | 156.5 | 154.8
Change from baseline | 17.29 | -8.22
Difference from placebo 95% CI |  | -25.51 (-49.55, -1.47 [Not evaluated for statistical significance, not part of sequential testing procedure.]

14.3 Cardiovascular Outcomes in Adults with Type 2 Diabetes Mellitus and Atherosclerotic Cardiovascular Disease

The CANVAS and CANVAS-R trials were multicenter, multi-national, randomized, double-blind parallel group, with similar inclusion and exclusion criteria. Patients eligible for enrollment in both CANVAS and CANVAS-R trials were: 30 years of age or older and had established, stable, cardiovascular, cerebrovascular, peripheral artery disease (66% of the enrolled population) or were 50 years of age or older and had two or more other specified risk factors for cardiovascular disease (34% of the enrolled population).

The integrated analysis of the CANVAS and CANVAS-R trials compared the risk of Major Adverse Cardiovascular Event (MACE) between canagliflozin and placebo when these were added to and used concomitantly with standard of care treatments for diabetes and atherosclerotic cardiovascular disease. The primary endpoint, MACE, was the time to first occurrence of a three-part composite outcome which included cardiovascular death, non-fatal myocardial infarction and non-fatal stroke.

In CANVAS, patients were randomly assigned 1:1:1 to canagliflozin 100 mg, canagliflozin 300 mg, or matching placebo. In CANVAS-R, patients were randomly assigned 1:1 to canagliflozin 100 mg or matching placebo, and titration to 300 mg was permitted at the investigator's discretion (based on tolerability and glycemic needs) after Week 13. Concomitant antidiabetic and atherosclerotic therapies could be adjusted, at the discretion of investigators, to ensure participants were treated according to the standard care for these diseases.

A total of 10,134 adult patients were treated (4,327 in CANVAS and 5,807 in CANVAS-R; total of 4,344 randomly assigned to placebo and 5,790 to canagliflozin) for a mean exposure duration of 149 weeks (223 weeks [4.3 years] in CANVAS and 94 weeks [1.8 years] in CANVAS-R).Approximately 78% of the trial population was White, 13% was Asian, and 3% was Black or African American. The mean age was 63 years and approximately 64% were male.

The mean HbA 1Cat baseline was 8.2% and mean duration of diabetes was 13.5 years with 70% of patients having had diabetes for 10 years or more. Approximately 31%, 21% and 17% reported a past history of neuropathy, retinopathy and nephropathy, respectively, and the mean eGFR 76 mL/min/1.73 m ^2. At baseline, patients were treated with one (19%) or more (80%) antidiabetic medications including metformin HCl (77%), insulin (50%), and sulfonylurea (43%).

At baseline, the mean systolic blood pressure was 137 mmHg, the mean diastolic blood pressure was 78 mmHg, the mean LDL was 89 mg/dL, the mean HDL was 46 mg/dL, and the mean urinary albumin to creatinine ratio (UACR) was 115 mg/g. At baseline, approximately 80% of patients were treated with renin angiotensin system inhibitors, 53% with beta-blockers, 13% with loop diuretics, 36% with non-loop diuretics, 75% with statins, and 74% with antiplatelet agents (mostly aspirin). During the trial, investigators could modify anti-diabetic and cardiovascular therapies to achieve local standard of care treatment targets with respect to blood glucose, lipid, and blood pressure. More patients receiving canagliflozin compared to placebo initiated anti-thrombotics (5.2% vs 4.2%) and statins (5.8% vs 4.8%) during the trial.

For the primary analysis, a stratified Cox proportional hazards model was used to test for non-inferiority against a pre-specified risk margin of 1.3 for the hazard ratio of MACE.

In the integrated analysis of CANVAS and CANVAS-R trials, canagliflozin reduced the risk of first occurrence of MACE. The estimated hazard ratio (95% CI) for time to first MACE was 0.86 (0.75, 0.97). Refer to Table 21. Vital status was obtained for 99.6% of patients across the trials. The Kaplan-Meier curve depicting time to first occurrence of MACE is shown in Figure 3.

Table 21: Treatment Effect for the Primary Composite Endpoint, MACE, and its Components in the Integrated Analysis of CANVAS and CANVAS-R Trials in Adults with Type 2 Diabetes Mellitus and Atherosclerotic Cardiovascular Disease [Intent-To-Treat Analysis Set]
 | Placebo N=4,347(%) | Canagliflozin N=5,795 (%) | Hazard ratio (95% C.I.) [Stratified Cox-proportional hazards model with treatment as a factor and stratified by the trial and by prior CV disease]
Composite of cardiovascular death, non-fatal myocardial infarction, non-fatal stroke (time to first occurrence) [P-value for superiority (2-sided) = 0.0158] , [Number and percentage of first events] , [Due to pooling of unequal randomization ratios, Cochran-Mantel-Haenszel weights were applied to calculate percentages] | 426 (10.4) | 585 (9.2) | 0.86 (0.75, 0.97)
Non-fatal myocardial infarction , | 159 (3.9) | 215 (3.4) | 0.85 (0.69, 1.05)
Non-fatal Stroke , | 116 (2.8) | 158 (2.5) | 0.90 (0.71, 1.15)
Cardiovascular Death , | 185 (4.6) | 268 (4.1) | 0.87 (0.72, 1.06)

Figure 3: Time to First Occurrence of MACE in Adults with Type 2 Diabetes Mellitus

14.4 Renal and Cardiovascular Outcomes in Adults with Diabetic Nephropathy and Albuminuria

The Canagliflozin and Renal Events in Diabetes with Established Nephropathy Clinical Evaluation Trial (CREDENCE) was a multinational, randomized, double-blind, placebo-controlled trial comparing canagliflozin with placebo in adult patients with type 2 diabetes mellitus, an eGFR ≥ 30 to < 90 mL/min/1.73 m ^2 and albuminuria (urine albumin/creatinine > 300 to ≤ 5,000 mg/g) who were receiving standard of care including a maximum-tolerated, labeled daily dose of an angiotensin-converting enzyme inhibitor (ACEi) or angiotensin receptor blocker (ARB).

The primary objective of CREDENCE was to assess the efficacy of canagliflozin relative to placebo in reducing the composite endpoint of end stage kidney disease (ESKD), doubling of serum creatinine, and renal or CV death.

Patients were randomized to receive canagliflozin 100 mg (N=2,202) or placebo (N=2,199) and treatment was continued until the initiation of dialysis or renal transplantation.

The median follow-up duration for the 4,401 randomized subjects was 137 weeks. Vital status was obtained for 99.9% of subjects.

The population was 67% White, 20% Asian, and 5% Black or African American; 32% were of Hispanic or Latino ethnicity. The mean age was 63 years and 66% were male.

At randomization, the mean HbA 1C was 8.3%, the median urine albumin/creatinine was 927 mg/g, the mean eGFR was 56.2 mL/min/1.73 m ^2, 50% had prior CV disease, and 15% reported a history of heart failure. The most frequent antihyperglycemic agents (AHA) medications used at baseline were insulin (66%), biguanides (58%), and sulfonylureas (29%). Nearly all subjects (99.9%) were on ACEi or ARB at randomization, approximately 60% were taking an anti-thrombotic agent (including aspirin), and 69% were on a statin.

The primary composite endpoint in the CREDENCE trial was the time to first occurrence of ESKD (defined as an eGFR < 15 mL/min/1.73 m ^2, initiation of chronic dialysis or renal transplant), doubling of serum creatinine, and renal or CV death. Canagliflozin 100 mg significantly reduced the risk of the primary composite endpoint based on a time-to-event analysis [HR: 0.70; 95% CI: 0.59, 0.82; p<0.0001] (see Figure 4). The treatment effect reflected a reduction in progression to ESKD, doubling of serum creatinine and cardiovascular death as shown in Table 22 and Figure 4. There were few renal deaths during the trial. Canagliflozin 100 mg also significantly reduced the risk of hospitalization for heart failure [HR: 0.61; 95% CI: 0.47 to 0.80; p<0.001].

Table 22: Analysis of Primary Endpoint (including the Individual Components) and Secondary Endpoints from the CREDENCE Trial in Adults with Diabetic Nephropathy and Albuminuria
 | Placebo |  | canagliflozin
Endpoint | N=2,199 (%) | Event Rate [Event rate per 100 patient-years.] | N=2,202 (%) | Event Rate | HR [Hazard ratio (canagliflozin compared to placebo), 95% CI and p-value are estimated using a stratified Cox proportional hazards model including treatment as the explanatory variable and stratified by screening eGFR (≥ 30 to < 45, ≥ 45 to < 60, ≥ 60 to < 90 mL/min/1.73 m 2). HR is not presented for renal death due to the small number of events in each group.] (95% CI)
Primary Composite Endpoint (ESKD, doubling of serum creatinine, renal death, or CV death) | 340 (15.5) | 6.1 | 245 (11.1) | 4.3 | 0.70 (0.59, 0.82) [P-value <0.0001]
ESKD | 165 (7.5) | 2.9 | 116 (5.3) | 2.0 | 0.68 (0.54, 0.86)
Doubling of serum creatinine | 188 (8.5) | 3.4 | 118 (5.4) | 2.1 | 0.60 (0.48, 0.76)
Renal death | 5 (0.2) | 0.1 | 2 (0.1) | 0.0
CV death | 140 (6.4) | 2.4 | 110 (5.0) | 1.9 | 0.78 (0.61, 1.00)
CV death or hospitalization for heart failure | 253 (11.5) | 4.5 | 179 (8.1) | 3.1 | 0.69 (0.57, 0.83) [P-value <0.001]
CV death, non-fatal myocardial infarction or non-fatal stroke | 269 (12.2) | 4.9 | 217 (9.9) | 3.9 | 0.80 (0.67, 0.95) [P-value <0.02]
Non-fatal myocardial infarction | 87 (4.0) | 1.6 | 71 (3.2) | 1.3 | 0.81 (0.59, 1.10)
Non-fatal stroke | 66 (3.0) | 1.2 | 53 (2.4) | 0.9 | 0.80 (0.56, 1.15)
Hospitalization for heart failure | 141 (6.4) | 2.5 | 89 (4.0) | 1.6 | 0.61 (0.47, 0.80)
ESKD, doubling of serum creatinine or renal death | 224 (10.2) | 4.0 | 153 (6.9) | 2.7 | 0.66 (0.53, 0.81)
Intent-To-Treat Analysis Set (time to first occurrence)
The individual components do not represent a breakdown of the composite outcomes, but rather the total number of subjects experiencing an event during the course of the trial.

The Kaplan-Meier curve (Figure 4) shows time to first occurrence of the primary composite endpoint of ESKD, doubling of serum creatinine, renal death, or CV death. The curves begin to separate by Week 52 and continue to diverge thereafter.

Figure 4: CREDENCE: Time to First Occurrence of the Primary Composite Endpoint

16 HOW SUPPLIED/STORAGE AND HANDLING

INVOKANA®(canagliflozin) tablets are available in the strengths and packages listed below:

100 mg tablets are yellow, capsule-shaped, film-coated tablets with "CFZ" on one side and "100" on the other side.

Bottles of approximately 2070 film-coated tablets, NDC 55154-1425-8

300 mg tablets are white, capsule-shaped, film-coated tablets with "CFZ" on one side and "300" on the other side.

Bottles of approximately 720 film-coated tablets, NDC 55154-1426-8

Storage and Handling
Keep out of reach of children.

Store at 20 °C to 25 °C (68 °F to 77 °F); excursions permitted between 15 °C to 30 °C (59 °F to 86 °F) [see USP Controlled Room Temperature].

17 PATIENT COUNSELING INFORMATION

Advise the patient to read the FDA-approved patient labeling (Medication Guide).

Diabetic Ketoacidosis in Patients with Type 1 Diabetes Mellitus and Other Ketoacidosis

Inform patients that INVOKANA can cause potentially fatal ketoacidosis and that type 2 diabetes mellitus and pancreatic disorders (e.g., history of pancreatitis or pancreatic surgery) are risk factors.

Educate all patients on precipitating factors (such as insulin dose reduction or missed doses, infection, reduced caloric intake, ketogenic diet, surgery, dehydration, and alcohol abuse) and symptoms of ketoacidosis (including nausea, vomiting, abdominal pain, tiredness, and labored breathing). Inform patients that blood glucose may be normal even in the presence of ketoacidosis.

Advise patients that they may be asked to monitor ketones. If symptoms of ketoacidosis occur, instruct patients to discontinue INVOKANA and seek medical attention immediately [see Warnings and Precautions (5.1)].

Lower Limb Amputation

Inform patients that INVOKANA is associated with an increased risk of amputations. Counsel patients about the importance of routine preventative foot care. Instruct patients to monitor for new pain or tenderness, sores or ulcers, or infections involving the leg or foot and to seek medical advice immediately if such signs or symptoms develop [see Warnings and Precautions (5.2)].

Volume Depletion

Inform patients that symptomatic hypotension may occur with INVOKANA and advise them to contact their doctor if they experience such symptoms [see Warnings and Precautions (5.3)]. Inform patients that dehydration may increase the risk for hypotension, and to have adequate fluid intake.

Hypoglycemia with Concomitant Use with Insulin or Insulin Secretagogues

Inform patients that hypoglycemia has been reported when INVOKANA is used with insulin or insulin secretagogues. Educate patients or caregivers on the signs and symptoms of hypoglycemia [see Warnings and Precautions (5.5)].

Serious Urinary Tract Infections

Inform patients of the potential for urinary tract infections, which may be serious. Provide them with information on the symptoms of urinary tract infections. Advise them to seek medical advice if such symptoms occur [see Warnings and Precautions (5.4)].

Necrotizing Fasciitis of the Perineum (Fournier's Gangrene)

Inform patients that necrotizing infections of the perineum (Fournier's gangrene) have occurred with INVOKANA. Counsel patients to promptly seek medical attention if they develop pain or tenderness, redness, or swelling of the genitals or the area from the genitals back to the rectum, along with a fever above 100.4°F or malaise [see Warnings and Precautions (5.6)].

Genital Mycotic Infections in Females (e.g., Vulvovaginitis)

Inform female patients that vaginal yeast infection may occur and provide them with information on the signs and symptoms of vaginal yeast infection. Advise them of treatment options and when to seek medical advice [see Warnings and Precautions (5.7)].

Genital Mycotic Infections in Males (e.g., Balanitis or Balanoposthitis)

Inform male patients that yeast infection of penis (e.g., balanitis or balanoposthitis) may occur, especially in uncircumcised males and patients with prior history. Provide them with information on the signs and symptoms of balanitis and balanoposthitis (rash or redness of the glans or foreskin of the penis). Advise them of treatment options and when to seek medical advice [see Warnings and Precautions (5.7)].

Hypersensitivity Reactions

Inform patients that serious hypersensitivity reactions, such as urticaria, rash, anaphylaxis, and angioedema, have been reported with INVOKANA. Advise patients to report immediately any signs or symptoms suggesting allergic reaction, and to discontinue drug until they have consulted prescribing physicians [see Warnings and Precautions (5.8)].

Bone Fracture

Inform patients that bone fractures have been reported in adult patients taking INVOKANA. Provide them with information on factors that may contribute to fracture risk [see Warnings and Precautions (5.9)].

Pregnancy

Advise pregnant women, and females of reproductive potential of the potential risk to a fetus with treatment with INVOKANA [see Use in Specific Populations (8.1)]. Instruct females of reproductive potential to report pregnancies to their physicians as soon as possible.

Lactation

Advise women that breastfeeding is not recommended during treatment with INVOKANA [see Use in Specific Populations (8.2)].

Laboratory Tests

Inform patients that due to its mechanism of action, patients taking INVOKANA will test positive for glucose in their urine [see Drug Interactions (7)].

Missed Dose

If a dose is missed, advise patients to take it as soon as it is remembered unless it is almost time for the next dose, in which case patients should skip the missed dose and take the medicine at the next regularly scheduled time. Advise patients not to take two doses of INVOKANA at the same time.

Active ingredient made in Belgium

Manufactured for:
Janssen Pharmaceuticals, Inc.
Titusville, NJ 08560, USA

Licensed from Mitsubishi Tanabe Pharma Corporation

For patent information: www.janssenpatents.com

© Johnson & Johnson and its affiliates 2013 – 2024

Distributed By:

Cardinal Health

Dublin, OH 43017

ER7296 Rev. C

ER7297 Rev. C

Medication Guide
INVOKANA® (in-vo-KAHN-uh)
(canagliflozin)
tablets, for oral use

What is the most important information I should know about INVOKANA?

INVOKANA can cause serious side effects, including:

- Diabetic ketoacidosis (increased ketones in your blood or urine) in people with type 1 and other ketoacidosis.INVOKANA can cause ketoacidosis that can be life-threatening and may lead to death. Ketoacidosis is a serious condition which needs to be treated in a hospital. People with type 1 diabetes have a high risk of getting ketoacidosis. People with type 2 diabetes or pancreas problems also have an increased risk of getting ketoacidosis. Ketoacidosis can also happen in people who: are sick, cannot eat or drink as usual, skip meals, are on a diet high in fat and low in carbohydrates (ketogenic diet), take less than the usual amount of insulin or miss insulin doses, drink too much alcohol, have a loss of too much fluid from the body (volume depletion), or who have surgery or a procedure that requires not having food for a long time (prolonged fasting). Ketoacidosis can happen even if your blood sugar is less than 250 mg/dL. Your healthcare provider may ask you to periodically check ketones in your urine or blood.
- Stop taking INVOKANA and call your healthcare provider or get medical help right away if you get any of the following. If possible, check for ketones in your urine or blood, even if your blood sugar is less than 250 mg/dL:

- nausea
- vomiting
- stomach-area (abdominal) pain

- tiredness
- trouble breathing
- ketones in your urine or blood

- Amputations. INVOKANA may increase your risk of lower limb amputations. Amputations mainly involve removal of the toe or part of the foot, however, amputations involving the leg, below and above the knee, have also occurred. Some people had more than one amputation, some on both sides of the body.
  You may be at a higher risk of lower limb amputation if you:
  - have a history of amputation
  - have heart disease or are at risk for heart disease
  - have had blocked or narrowed blood vessels, usually in your leg
  - have damage to the nerves (neuropathy) in your leg
  - have had diabetic foot ulcers or sores

Call your healthcare provider right away if you have new pain or tenderness, any sores, ulcers, or infections in your leg or foot. Your healthcare provider may decide to stop your INVOKANA for a while if you have any of these signs or symptoms.

Talk to your healthcare provider about proper foot care.

- Dehydration. INVOKANA can cause some people to become dehydrated (the loss of too much body water). Dehydration may cause you to feel dizzy, faint, lightheaded, or weak, especially when you stand up (orthostatic hypotension). There have been reports of sudden worsening of kidney function in people with type 2 diabetes who are taking INVOKANA.
  You may be at higher risk of dehydration if you:
  - take medicines to lower your blood pressure, including diuretics (water pill)
  - are on a low sodium (salt) diet
  - have kidney problems
  - are 65 years of age or older

Talk to your healthcare provider about what you can do to prevent dehydration including how much fluid you should drink on a daily basis. Call your healthcare provider right away if you reduce the amount of food or liquid you drink, for example if you cannot eat or you start to lose liquids from your body, for example from vomiting, diarrhea, or being in the sun too long.

- Vaginal yeast infection.Women who take INVOKANA may get vaginal yeast infections. Yeast infections can be a serious but common side effect of INVOKANA. Symptoms of a vaginal yeast infection include:
  - vaginal odor
  - white or yellowish vaginal discharge (discharge may be lumpy or look like cottage cheese)
  - vaginal itching
- Yeast infection of the skin around the penis (balanitis or balanoposthitis).Men who take INVOKANA may get a yeast infection of the skin around the penis. Men who are not circumcised may have swelling of the penis that makes it difficult to pull back the skin around the tip of the penis. Other symptoms of yeast infection of the penis include:

- redness, itching, or swelling of the penis
- foul smelling discharge from the penis

- rash of the penis
- pain in the skin around penis

Talk to your healthcare provider about what to do if you get symptoms of a yeast infection of the vagina or penis. Your healthcare provider may suggest you use an over-the-counter antifungal medicine. Talk to your healthcare provider right away if you use an over-the-counter antifungal medication and your symptoms do not go away.

What is INVOKANA?

- INVOKANA is a prescription medicine used:
  - along with diet and exercise to lower blood sugar (glucose) in adults and children aged 10 years and older with type 2 diabetes.
  - to reduce the risk of major cardiovascular events such as heart attack, stroke or death in adults with type 2 diabetes who have known cardiovascular disease.
  - to reduce the risk of end stage kidney disease (ESKD), worsening of kidney function, cardiovascular death, and hospitalization for heart failure in adults with type 2 diabetes and diabetic kidney disease (nephropathy) with a certain amount of protein in the urine.
- INVOKANA is not recommended to decrease blood sugar (glucose) in people with type 1 diabetes.
- INVOKANA is not recommended to decrease blood sugar (glucose) in people with type 2 diabetes with severe kidney problems.
- It is not known if INVOKANA is safe and effective in children under 10 years of age.

Do not take INVOKANA if you:

- are allergic to canagliflozin or any of the ingredients in INVOKANA. See the end of this Medication Guide for a list of ingredients in INVOKANA. Symptoms of allergic reaction to INVOKANA may include:
  - rash
  - raised red patches on your skin (hives)
  - swelling of the face, lips, mouth, tongue, and throat that may cause difficulty in breathing or swallowing

Before taking INVOKANA, tell your healthcare provider about all of your medical conditions, including if you:

- have type 1 diabetes or have had diabetic ketoacidosis.
- have a decrease in your insulin dose.
- have a serious infection.
- have a history of infection of the vagina or penis.
- have a history of amputation.
- have had blocked or narrowed blood vessels, usually in your leg.
- have damage to the nerves (neuropathy) in your leg.
- have had diabetic foot ulcers or sores.
- have kidney problems.
- have liver problems.
- have a history of urinary tract infections or problems with urination.
- are on a low sodium (salt) diet. Your healthcare provider may change your diet or your dose of INVOKANA.
- are going to have surgery or a procedure that requires not having food for a long time (prolonged fasting). Your healthcare provider may stop your INVOKANA before you have surgery. Talk to your healthcare provider if you are having surgery about when to stop taking INVOKANA and when to start it again.
- are eating less or there is a change in your diet.
- are dehydrated.
- have or have had problems with your pancreas, including pancreatitis or surgery on your pancreas.
- drink alcohol very often, or drink a lot of alcohol in the short-term ("binge" drinking).
- have ever had an allergic reaction to INVOKANA.
- are pregnant or plan to become pregnant. INVOKANA may harm your unborn baby. If you become pregnant while taking INVOKANA, tell your healthcare provider as soon as possible. Talk with your healthcare provider about the best way to control your blood sugar while you are pregnant.
- are breastfeeding or plan to breastfeed. INVOKANA may pass into your breast milk and may harm your baby. Talk with your healthcare provider about the best way to feed your baby if you are taking INVOKANA. Do not breastfeed while taking INVOKANA.

Tell your healthcare provider about all the medicines you take, including prescription and over-the-counter medicines, vitamins, and herbal supplements.

INVOKANA may affect the way other medicines work, and other medicines may affect how INVOKANA works. Know the medicines you take. Keep a list of them and show it to your healthcare provider and pharmacist when you get a new medicine.

How should I take INVOKANA?

- Take INVOKANA by mouth 1 time each day exactly as your healthcare provider tells you to take it.
- Your healthcare provider will tell you how much INVOKANA to take and when to take it. Your healthcare provider may change your dose if needed.
- It is best to take INVOKANA before the first meal of the day.
- Your healthcare provider may tell you to take INVOKANA along with other diabetes medicines. Low blood sugar can happen more often when INVOKANA is taken with certain other diabetes medicines. See " What are the possible side effects of INVOKANA?"
- Your healthcare provider may tell you to stop taking INVOKANA at least 3 days before any surgery or procedure that requires not having food or water for a long time (prolonged fasting).
- If you miss a dose, take it as soon as you remember. If it is almost time for your next dose, skip the missed dose and take the medicine at the next regularly scheduled time. Do not take two doses of INVOKANA at the same time. Talk to your healthcare provider if you have questions about a missed dose.
- If you take too much INVOKANA, call your healthcare provider or Poison Help line at 1-800-222-1222 or go to the nearest hospital emergency room right away.
- When your body is under some types of stress, such as fever, trauma (such as a car accident), infection, or surgery, the amount of diabetes medicine you need may change. Tell your healthcare provider right away if you have any of these conditions and follow your healthcare provider's instructions.
- INVOKANA will cause your urine to test positive for glucose.
- Your healthcare provider may do certain blood tests before you start INVOKANA and during treatment as needed. Your healthcare provider may change your dose of INVOKANA based on the results of your blood tests.

What are the possible side effects of INVOKANA?

INVOKANA may cause serious side effects including:

See " What is the most important information I should know about INVOKANA?"

- serious urinary tract infections.Serious urinary tract infections that may lead to hospitalization have happened in people who are taking INVOKANA. Tell your healthcare provider if you have any signs or symptoms of a urinary tract infection such as a burning feeling when passing urine, a need to urinate often, the need to urinate right away, pain in the lower part of your stomach (pelvis), or blood in the urine. Sometimes people may also have a fever, back pain, nausea, or vomiting.
- low blood sugar (hypoglycemia).If you take INVOKANA with another medicine that can cause low blood sugar, such as a sulfonylurea or insulin, your risk of getting low blood sugar is higher. The dose of your sulfonylurea medicine or insulin may need to be lowered while you take INVOKANA.
  Signs and symptoms of low blood sugar may include:

- headache
- confusion
- hunger
- shaking or feeling jittery

- drowsiness
- dizziness
- fast heartbeat

- weakness
- irritability
- sweating

- a rare but serious bacterial infection that causes damage to the tissue under the skin (necrotizing fasciitis) in the area between and around the anus and genitals (perineum).Necrotizing fasciitis of the perineum has happened in people who take INVOKANA. Necrotizing fasciitis of the perineum may lead to hospitalization, may require multiple surgeries, and may lead to death. Seek medical attention immediately if you have fever or you are feeling very weak, tired or uncomfortable (malaise) and you develop any of the following symptoms in the area between and around your anus and genitals:

- pain or tenderness

- swelling

- redness of the skin (erythema)

- serious allergic reaction.If you have any symptoms of a serious allergic reaction, stop taking INVOKANA and call your healthcare provider right away or go to the nearest hospital emergency room. See "Do not take INVOKANA if you:". Your healthcare provider may give you a medicine for your allergic reaction and prescribe a different medicine for your diabetes.
- broken bones (fractures).Bone fractures have been seen in patients taking INVOKANA. Talk to your healthcare provider about factors that may increase your risk of bone fracture.

The most common side effects of INVOKANA include:

- vaginal yeast infections and yeast infections of the penis (See "What is the most important information I should know about INVOKANA?")
- changes in urination, including urgent need to urinate more often, in larger amounts, or at night

These are not all the possible side effects of INVOKANA.

Call your doctor for medical advice about side effects. You may report side effects to FDA at 1-800-FDA-1088.

You may also report side effects to Janssen Pharmaceuticals, Inc. at 1-800-526-7736.

How should I store INVOKANA?

- Store INVOKANA at room temperature between 68 °F to 77 °F (20 °C to 25 °C).
- Keep INVOKANA and all medicines out of the reach of children.

General information about the safe and effective use of INVOKANA.

Medicines are sometimes prescribed for purposes other than those listed in a Medication Guide. Do not use INVOKANA for a condition for which it was not prescribed. Do not give INVOKANA to other people, even if they have the same symptoms that you have. It may harm them.

You can ask your pharmacist or healthcare provider for information about INVOKANA that is written for health professionals.

What are the ingredients in INVOKANA?

Active ingredient: canagliflozin

Inactive ingredients: croscarmellose sodium (E468), hydroxypropyl cellulose (E463), lactose anhydrous, magnesium stearate (E572), and microcrystalline cellulose (E460[i]). In addition, the tablet coating contains iron oxide yellow (E172) (100 mg tablet only), macrogol/PEG3350 (E1521), polyvinyl alcohol (E1203) (partially hydrolyzed), talc (E553b), and titanium dioxide (E171).

Active ingredient made in Belgium. Manufactured for: Janssen Pharmaceuticals, Inc., Titusville, NJ 08560, USA.
Licensed from Mitsubishi Tanabe Pharma Corporation. For patent information: www.janssenpatents.com © Johnson & Johnson and its affiliates 2013 – 2024
For more information about INVOKANA, call 1-800-526-7736 or visit our website at www.invokana.com.

Distributed By:

Cardinal Health

Dublin, OH 43017

ER7296 Rev. C

ER7297 Rev. C

This Medication Guide has been approved by the U.S. Food and Drug Administration.

Revised: 12/2024

Package/Label Display Panel

Contains Approximately

2070 Tablets

INVOKANA®

(canagliflozin) tablets

100 mg

Each tablet contains:

100 mg canagliflozin.

Attention: Dispense the Medication

Guide to each patient.

Rx Only

WARNING: Keep out of reach of

children.

Package/Label Display Panel

Contains Approximately

720 Tablets

INVOKANA®

(canagliflozin) tablets

300 mg

Each tablet contains:

300 mg canagliflozin.

Attention: Dispense with Medication

Guide to each patient.

Rx Only

WARNING: Keep out of reach of

children.